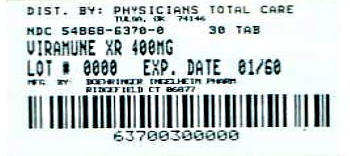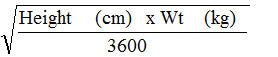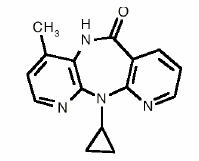 DRUG LABEL: Viramune
NDC: 54868-6370 | Form: TABLET, EXTENDED RELEASE
Manufacturer: Physicians Total Care, Inc.
Category: prescription | Type: HUMAN PRESCRIPTION DRUG LABEL
Date: 20130206

ACTIVE INGREDIENTS: NEVIRAPINE 400 mg/1 1

HIGHLIGHTS OF PRESCRIBING INFORMATION

These highlights do not include all the information needed to use VIRAMUNE XR safely and effectively. See full prescribing information for VIRAMUNE XR.
Viramune XR® (nevirapine) Extended-Release Tablets, for oral use
Initial U.S. Approval: 1996

RECENT MAJOR CHANGES

Indications and Usage (1) |  | 11/2012
Dosage and Administration
General Dosing Considerations (2.1) |  | 11/2012
Pediatric Patients (2.3) |  | 11/2012
Dosage Adjustment (2.5) |  | 11/2012
Warnings and Precautions
Immune Reconstitution Syndrome (5.5) |  | 11/2012

WARNING: LIFE-THREATENING (INCLUDING FATAL) HEPATOTOXICITY and SKIN REACTIONS

See full prescribing information for complete boxed warning.

- Fatal and non-fatal hepatotoxicity (5.1)
- Fatal and non-fatal skin reactions (5.2)

Discontinue immediately if experiencing:

- Signs or symptoms of hepatitis (5.1)
- Increased transaminases combined with rash or other systemic symptoms (5.1)
- Severe skin or hypersensitivity reactions (5.2)
- Any rash with systemic symptoms (5.2)

Monitoring during the first 18 weeks of therapy is essential. Extra vigilance is warranted during the first 6 weeks of therapy, which is the period of greatest risk of these events (5).

1 INDICATIONS AND USAGE

- VIRAMUNE XR is an NNRTI indicated for combination antiretroviral treatment of HIV-1 infection in adults and in children 6 to less than 18 years of age. (1)

Important Considerations:

- Initiation of treatment is not recommended in the following populations unless the benefits outweigh the risks. (1, 5.1)
  - adult females with CD4^+ cell counts greater than 250 cells/mm^3
  - adult males with CD4^+ cell counts greater than 400 cells/mm^3
- The 14-day lead-in period with immediate-release VIRAMUNE (200 mg once daily) must be strictly followed; it has been demonstrated to reduce the frequency of rash. (2.5, 5.2)

2 DOSAGE AND ADMINISTRATION

- The VIRAMUNE XR tablets must be swallowed whole and must not be chewed, crushed, or divided (2.1)
- Adult patients must initiate therapy with one 200 mg tablet of immediate-release VIRAMUNE once daily for the first 14 days, followed by one 400 mg tablet of VIRAMUNE XR once daily. (2.2)
- Adult patients already on a regimen of immediate-release VIRAMUNE twice daily can be switched to VIRAMUNE XR 400 mg once daily without the 14-day lead-in period of immediate-release VIRAMUNE. (2.2)
- Pediatric patients (ages 6 to less than18 years) must initiate therapy with immediate-release VIRAMUNE (as 150 mg/m^2 of VIRAMUNE Oral Suspension or as VIRAMUNE tablet) at a dose not to exceed 200 mg per day administered once daily for the first 14 days, followed by VIRAMUNE XR once daily as shown in the following table. (2.3)
  Recommended Dosing for Pediatric Patients 6 to less than 18 years of age by BSA after the Lead-in Period
  BSA range (m^2) | VIRAMUNE XR tablets dose (mg)
  0.58 - 0.83 | 200 mg once daily (2 x 100 mg)
  0.84 - 1.16 | 300 mg once daily (3 x 100 mg)
  Greater than or equal to 1.17 | 400 mg once daily (1 x 400 mg)
- Pediatric patients already on a regimen of twice-daily VIRAMUNE Oral Suspension or immediate-release VIRAMUNE can be switched to VIRAMUNE XR once daily without the 14-day lead-in period of VIRAMUNE Oral Suspension or immediate-release VIRAMUNE. (2.3)
- If any patient experiences rash during the 14-day lead-in period with immediate-release VIRAMUNE do not initiate VIRAMUNE XR until the rash has resolved. Do not continue the immediate-release VIRAMUNE lead-in dosing regimen beyond 28 days. (2.5)
- If dosing is interrupted for greater than 7 days, restart 14-day lead-in dosing. (2.5)

3 DOSAGE FORMS AND STRENGTHS

- 100 mg and 400 mg tablets (3)

4 CONTRAINDICATIONS

- Patients with moderate or severe (Child-Pugh Class B or C, respectively) hepatic impairment. (4.1, 5.1, 8.7)
- Use as part of occupational and non-occupational post-exposure prophylaxis (PEP) regimens, an unapproved use. (4.2, 5.1)

5 WARNINGS AND PRECAUTIONS

- Hepatotoxicity: Fatal and non-fatal hepatotoxicity has been reported. Monitor liver function tests before and during therapy. Permanently discontinue nevirapine if clinical hepatitis or transaminase elevations combined with rash or other systemic symptoms occur. Do not restart nevirapine after recovery. (5.1)
- Rash: Fatal and non-fatal skin reactions, including Stevens-Johnson syndrome, toxic epidermal necrolysis, and hypersensitivity reactions, have been reported. Permanently discontinue nevirapine if severe skin reactions or hypersensitivity reactions occur. Check transaminase levels immediately for all patients who develop a rash in the first 18 weeks of treatment. (5.2)
- Monitor patients for immune reconstitution syndrome and fat redistribution. (5.5, 5.6)

6 ADVERSE REACTIONS

- Adult patients: The most common adverse reaction is rash. During the lead-in period with immediate-release VIRAMUNE, the incidence of Grade 2 or higher drug-related rash in adults is 3%. After the lead-in period the incidence of Grade 2 or higher drug-related rash in subjects taking VIRAMUNE XR is 3%. The incidence of Grade 2 or higher drug-related clinical hepatitis after the lead-in phase was 2%. (6.1)
- Pediatric patients: The incidence of Grade 2 or higher drug-related rash was 1%. (6.2)

To report SUSPECTED ADVERSE REACTIONS, contact Boehringer Ingelheim Pharmaceuticals, Inc. at (800) 542-6257 or (800) 459-9906 TTY, or FDA at 1-800-FDA-1088 or www.fda.gov/medwatch.

7 DRUG INTERACTIONS

Co-administration of VIRAMUNE XR can alter the concentrations of other drugs, and other drugs may alter the concentration of nevirapine. The potential for drug interactions must be considered prior to and during therapy. (5.4, 7, 12.3)

8 USE IN SPECIFIC POPULATIONS

- No dose adjustment is required for patients with renal impairment with a creatinine clearance greater than or equal to 20 mL per min. Patients on dialysis receive an additional dose of immediate-release VIRAMUNE (200 mg) following each dialysis treatment (2.5, 8.6)
- Monitor patients with hepatic fibrosis or cirrhosis carefully for evidence of drug induced toxicity. Do not administer VIRAMUNE XR to patients with Child-Pugh B or C. (5.1, 8.7)

FULL PRESCRIBING INFORMATION

WARNING: LIFE-THREATENING (INCLUDING FATAL) HEPATOTOXICITY and SKIN REACTIONS

HEPATOTOXICITY:

Severe, life-threatening, and in some cases fatal hepatotoxicity, particularly in the first 18 weeks, has been reported in patients treated with nevirapine. In some cases, patients presented with non-specific prodromal signs or symptoms of hepatitis and progressed to hepatic failure. These events are often associated with rash. Female gender and higher CD4^+ cell counts at initiation of therapy place patients at increased risk; women with CD4^+ cell counts greater than 250 cells/mm^3, including pregnant women receiving nevirapine in combination with other antiretrovirals for the treatment of HIV-1 infection, are at the greatest risk. However, hepatotoxicity associated with nevirapine use can occur in both genders, all CD4^+ cell counts and at any time during treatment. Hepatic failure has also been reported in patients without HIV taking nevirapine for post-exposure prophylaxis (PEP). Use of nevirapine for occupational and non-occupational PEP is contraindicated [see Contraindications (4.2)]. Patients with signs or symptoms of hepatitis, or with increased transaminases combined with rash or other systemic symptoms, must discontinue nevirapine and seek medical evaluation immediately [see Warnings and Precautions (5.1)].

SKIN REACTIONS:

Severe, life-threatening skin reactions, including fatal cases, have occurred in patients treated with nevirapine. These have included cases of Stevens-Johnson syndrome, toxic epidermal necrolysis, and hypersensitivity reactions characterized by rash, constitutional findings, and organ dysfunction. Patients developing signs or symptoms of severe skin reactions or hypersensitivity reactions must discontinue nevirapine and seek medical evaluation immediately. Transaminase levels should be checked immediately for all patients who develop a rash in the first 18 weeks of treatment. The 14-day lead-in period with immediate-release VIRAMUNE 200 mg daily dosing has been observed to decrease the incidence of rash and must be followed [see Warnings and Precautions (5.2)].

MONITORING:

Patients must be monitored intensively during the first 18 weeks of therapy with nevirapine to detect potentially life-threatening hepatotoxicity or skin reactions. Extra vigilance is warranted during the first 6 weeks of therapy, which is the period of greatest risk of these events. Do not restart nevirapine following clinical hepatitis, or transaminase elevations combined with rash or other systemic symptoms, or following severe skin rash or hypersensitivity reactions. In some cases, hepatic injury has progressed despite discontinuation of treatment.

1 INDICATIONS AND USAGE

VIRAMUNE XR is indicated for use in combination with other antiretroviral agents for the treatment of HIV-1 infection in adults and in children 6 to less than 18 years of age [see Clinical Studies (14.1, 14.2)].

Additional important information regarding the use of VIRAMUNE XR for the treatment of HIV-1 infection:

- Based on serious and life-threatening hepatotoxicity observed in controlled and uncontrolled trials, nevirapine should not be initiated in adult females with CD4^+ cell counts greater than 250 cells/mm^3 or in adult males with CD4^+ cell counts greater than 400 cells/mm^3 unless the benefit outweighs the risk [see Boxed Warning and Warnings and Precautions (5.1)].
- The 14-day lead-in period with immediate-release VIRAMUNE dosing must be strictly followed; it has been demonstrated to reduce the frequency of rash [see Dosage and Administration (2.5) and Warnings and Precautions (5.2)].
- If rash persists beyond the 14-day lead-in period with immediate-release VIRAMUNE, do not begin dosing with VIRAMUNE XR. The lead-in dosing with 200 mg once-daily immediate-release VIRAMUNE should not be continued beyond 28 days, at which point an alternative regimen should be sought.

2 DOSAGE AND ADMINISTRATION

2.1 General Dosing Considerations

- VIRAMUNE XR tablets must be swallowed whole and must not be chewed, crushed, or divided.
- Children should be assessed for their ability to swallow tablets before prescribing VIRAMUNE XR tablets.
- VIRAMUNE XR can be taken with or without food.
- No recommendations can be made regarding substitution of four VIRAMUNE XR 100 mg tablets for one VIRAMUNE XR 400 mg tablet.

2.2 Adult Patients

Patients not currently taking immediate-release VIRAMUNE

Patients must initiate therapy with one 200 mg tablet of immediate-release VIRAMUNE daily for the first 14 days in combination with other antiretroviral agents (this lead-in period should be used because it has been found to lessen the frequency of rash), followed by one 400 mg tablet of VIRAMUNE XR once daily.

Switching Patients from immediate-release VIRAMUNE to VIRAMUNE XR

Patients already on a regimen of immediate-release VIRAMUNE twice daily in combination with other antiretroviral agents can be switched to VIRAMUNE XR 400 mg once daily in combination with other antiretroviral agents without the 14-day lead-in period of immediate-release VIRAMUNE.

2.3 Pediatric Patients

Pediatric patients may be dosed using VIRAMUNE XR 400 mg or 100 mg tablets. VIRAMUNE XR is dosed based on a patient’s body surface area (BSA) calculated using the Mosteller formula. All pediatric patients must initiate therapy with immediate-release VIRAMUNE (as 150 mg/m^2 of VIRAMUNE Oral Suspension or as VIRAMUNE tablets), at a dose not to exceed 200 mg per day, administered once daily for the first 14 days. This lead-in period should be used because it has been demonstrated to reduce the frequency of rash. This lead-in period is not required if the patient is already on a regimen of twice daily immediate-release formulation in combination with other antiretroviral agents.

The recommended oral doses of VIRAMUNE XR for pediatric patients 6 to less than 18 years of age based upon their BSA are described in the table below. The total daily dose should not exceed 400 mg for any patient.

Table 1 Recommended VIRAMUNE XR Dosing for Pediatric Patients 6 to less than 18 years of age by BSA after the Lead-in Period with Immediate-Release VIRAMUNE
BSA range (m^2) | VIRAMUNE XR tablets dose (mg)
0.58 - 0.83 | 200 mg once daily (2 x 100 mg)
0.84 - 1.16 | 300 mg once daily (3 x 100 mg)
Greater than or equal to 1.17 | 400 mg once daily (1 x 400 mg)

Mosteller Formula: BSA (m^2) =

2.4 Monitoring of Patients

Intensive clinical and laboratory monitoring, including liver enzyme tests, is essential at baseline and during the first 18 weeks of treatment with nevirapine. The optimal frequency of monitoring during this period has not been established. Some experts recommend clinical and laboratory monitoring more often than once per month, and in particular, would include monitoring of liver enzyme tests prior to beginning the 14-day lead-in period with immediate-release VIRAMUNE, prior to initiation of VIRAMUNE XR, and at two weeks after initiation of VIRAMUNE XR therapy. After the initial 18-week period, frequent clinical and laboratory monitoring should continue throughout VIRAMUNE XR treatment [see Warnings and Precautions (5)]. In some cases, hepatic injury has progressed despite discontinuation of treatment.

Patients already on a regimen of immediate-release VIRAMUNE twice daily who switch to VIRAMUNE XR once daily should continue with their ongoing clinical and laboratory monitoring.

2.5 Dosage Adjustment

Patients with Rash

Discontinue nevirapine if a patient experiences severe rash or any rash accompanied by constitutional findings [see Boxed Warning, Warnings and Precautions (5.2), and Patient Counseling Information (17.1)]. Do not initiate therapy with VIRAMUNE XR if a patient experiences mild to moderate rash without constitutional symptoms during the 14-day lead-in period of immediate-release VIRAMUNE until the rash has resolved [see Warnings and Precautions (5.2) and Patient Counseling Information (17.1)]. The total duration of the once daily lead-in dosing period should not exceed 28 days at which point an alternative regimen should be sought.

Patients with Hepatic Events

If a clinical (symptomatic) hepatic event occurs, permanently discontinue nevirapine. Do not restart nevirapine after recovery [see Warnings and Precautions (5.1)].

Patients with Dose Interruption

For patients who interrupt VIRAMUNE XR dosing for more than 7 days, restart the recommended lead-in dosing with immediate-release VIRAMUNE, using one 200 mg tablet daily for the first 14 days.

Patients with Renal Impairment

Patients with CrCL greater than or equal to 20 mL per min and not requiring dialysis do not require an adjustment in dosing. The pharmacokinetics of nevirapine have not been evaluated in patients with CrCL less than 20 mL per min. An additional 200 mg dose of immediate-release VIRAMUNE following each dialysis treatment is indicated in patients requiring dialysis. Nevirapine metabolites may accumulate in patients receiving dialysis; however, the clinical significance of this accumulation is not known [see Clinical Pharmacology (12.3)]. VIRAMUNE XR has not been studied in patients with renal dysfunction.

3 DOSAGE FORMS AND STRENGTHS

VIRAMUNE XR Tablets
100 mg, yellow, round, biconvex extended-release tablets, debossed with “V01” on one side and the Boehringer Ingelheim logo on the other side.

400 mg, yellow, oval, biconvex extended-release tablets, debossed with “V04” on one side and the Boehringer Ingelheim logo on the other side.

4 CONTRAINDICATIONS

4.1 Hepatic Impairment

VIRAMUNE XR is contraindicated in patients with moderate or severe (Child-Pugh Class B or C, respectively) hepatic impairment [see Warnings and Precautions (5.1) and Use in Specific Populations (8.7)].

4.2 Post-Exposure Prophylaxis

VIRAMUNE XR is contraindicated for use as part of occupational and non-occupational post-exposure prophylaxis (PEP) regimens [see Warnings and Precautions (5.1)].

5 WARNINGS AND PRECAUTIONS

The most serious adverse reactions associated with nevirapine are hepatitis/hepatic failure, Stevens-Johnson syndrome, toxic epidermal necrolysis, and hypersensitivity reactions. Hepatitis/hepatic failure may be associated with signs of hypersensitivity which can include severe rash or rash accompanied by fever, general malaise, fatigue, muscle or joint aches, blisters, oral lesions, conjunctivitis, facial edema, eosinophilia, granulocytopenia, lymphadenopathy, or renal dysfunction.

The first 18 weeks of therapy with nevirapine are a critical period during which intensive clinical and laboratory monitoring of patients is required to detect potentially life-threatening hepatic events and skin reactions. The optimal frequency of monitoring during this time period has not been established. Some experts recommend clinical and laboratory monitoring more often than once per month, and in particular, include monitoring of liver enzyme tests prior to beginning the 14-day lead-in period with immediate-release VIRAMUNE, prior to initiation of VIRAMUNE XR (during the lead-in period), and at two weeks after initiation of VIRAMUNE XR therapy. After the initial 18-week period, frequent clinical and laboratory monitoring should continue throughout VIRAMUNE XR treatment. In addition, the 14-day lead-in period with immediate-release VIRAMUNE has been demonstrated to reduce the frequency of rash [see Dosage and Administration (2.2, 2.5)].

Patients already on a regimen of immediate-release VIRAMUNE twice daily who switch to VIRAMUNE XR therapy should continue with their ongoing clinical and laboratory monitoring.

5.1 Hepatotoxicity and Hepatic Impairment

Severe, life-threatening, and in some cases fatal hepatotoxicity, including fulminant and cholestatic hepatitis, hepatic necrosis and hepatic failure, have been reported in patients treated with nevirapine.

The risk of symptomatic hepatic events regardless of severity is greatest in the first 6 weeks of therapy. The risk continued to be greater in the nevirapine groups in controlled clinical trials through 18 weeks of treatment. However, hepatic events may occur at any time during treatment. In some cases, patients presented with non-specific, prodromal signs or symptoms of fatigue, malaise, anorexia, nausea, jaundice, liver tenderness or hepatomegaly, with or without initially abnormal serum transaminase levels. Rash was observed in approximately half of the patients with symptomatic hepatic adverse events. Fever and flu-like symptoms accompanied some of these hepatic events. Some events, particularly those with rash and other symptoms, have progressed to hepatic failure with transaminase elevation, with or without hyperbilirubinemia, hepatic encephalopathy, prolonged partial thromboplastin time, or eosinophilia. Rhabdomyolysis has been observed in some patients experiencing skin and/or liver reactions associated with nevirapine use. Patients with signs or symptoms of hepatitis must be advised to discontinue nevirapine and immediately seek medical evaluation, which should include liver enzyme tests.

Transaminases should be checked immediately if a patient experiences signs or symptoms suggestive of hepatitis and/or hypersensitivity reaction. Transaminases should also be checked immediately for all patients who develop a rash in the first 18 weeks of treatment. Physicians and patients should be vigilant for the appearance of signs or symptoms of hepatitis, such as fatigue, malaise, anorexia, nausea, jaundice, bilirubinuria, acholic stools, liver tenderness, or hepatomegaly. The diagnosis of hepatotoxicity should be considered in this setting, even if transaminases are initially normal or alternative diagnoses are possible [see Boxed Warning, Dosage and Administration (2.4), and Patient Counseling Information (17.1)].

If clinical hepatitis or transaminase elevations combined with rash or other systemic symptoms occur, permanently discontinue nevirapine. Do not restart nevirapine after recovery. In some cases, hepatic injury progresses despite discontinuation of treatment.

The patients at greatest risk of hepatic events, including potentially fatal events, are women with high CD4^+ cell counts. In a retrospective analysis of pooled clinical trials with immediate-release VIRAMUNE, during the first 6 weeks of treatment women had a 3-fold higher risk than men for symptomatic, often rash-associated, hepatic events (6% versus 2%). Patients with higher CD4^+ cell counts at initiation of nevirapine therapy are at higher risk for symptomatic hepatic events. Women with CD4^+ cell counts greater than 250 cells/mm^3 had a 12-fold higher risk of symptomatic hepatic adverse events compared to women with CD4^+ cell counts less than 250 cells/mm^3 (11% versus 1%). An increased risk was observed in men with CD4^+ cell counts greater than 400 cells/mm^3 (6% versus 1% for men with CD4^+ cell counts less than 400 cells/mm^3). However, all patients, regardless of gender, CD4^+ cell count, or antiretroviral treatment history, should be monitored for hepatotoxicity since symptomatic hepatic adverse events have been reported at all CD4^+ cell counts. Co-infection with hepatitis B or C and/or increased transaminase elevations at the start of therapy with nevirapine are associated with a greater risk of later symptomatic events (6 weeks or more after starting nevirapine) and asymptomatic increases in AST or ALT.

In addition, serious hepatotoxicity (including liver failure requiring transplantation in one instance) has been reported in HIV-1 uninfected individuals receiving multiple doses of immediate-release VIRAMUNE in the setting of post-exposure prophylaxis (PEP), an unapproved use. Use of VIRAMUNE XR for occupational and non-occupational PEP is contraindicated [see Contraindications (4.2)].

Increased nevirapine trough concentrations have been observed in some patients with hepatic fibrosis or cirrhosis. Therefore, carefully monitor patients with either hepatic fibrosis or cirrhosis for evidence of drug-induced toxicity. Do not administer nevirapine to patients with moderate or severe (Child-Pugh Class B or C, respectively) hepatic impairment [see Contraindications (4.1), Use in Specific Populations (8.7), and Clinical Pharmacology (12.3)]. VIRAMUNE XR has not been evaluated in subjects with hepatic impairment.

5.2 Skin Reactions

Severe and life-threatening skin reactions, including fatal cases, have been reported in patients taking nevirapine. These have occurred most frequently during the first 6 weeks of therapy. These have included cases of Stevens-Johnson syndrome, toxic epidermal necrolysis, and hypersensitivity reactions characterized by rash, constitutional findings, and organ dysfunction including hepatic failure. Rhabdomyolysis has been observed in some patients experiencing skin and/or liver reactions associated with nevirapine use.

Patients developing signs or symptoms of severe skin reactions or hypersensitivity reactions (including, but not limited to, severe rash or rash accompanied by fever, general malaise, fatigue, muscle or joint aches, blisters, oral lesions, conjunctivitis, facial edema, and/or hepatitis, eosinophilia, granulocytopenia, lymphadenopathy, and renal dysfunction) must permanently discontinue nevirapine and seek medical evaluation immediately [see Boxed Warning and Patient Counseling Information (17.1)]. Do not restart nevirapine following severe skin rash, skin rash combined with increased transaminases or other symptoms, or hypersensitivity reaction.

If patients present with a suspected nevirapine-associated rash, measure transaminases immediately. Permanently discontinue nevirapine in patients with rash-associated transaminase elevations [see Warnings and Precautions (5.1)].

Patients must initiate therapy with immediate-release VIRAMUNE daily for the first 14 days. This lead-in period has been shown to reduce the frequency of rash. Discontinue nevirapine if a patient experiences severe rash or any rash accompanied by constitutional findings. Do not initiate VIRAMUNE XR if a patient experiencing a mild to moderate rash without constitutional symptoms during the 14-day immediate-release VIRAMUNE lead-in period of 200 mg/day (150 mg/m^2/day in pediatric patients) until the rash has resolved. The total duration of the immediate-release VIRAMUNE lead-in dosing period must not exceed 28 days at which point an alternative regimen should be sought [see Dosage and Administration (2.5)]. Patients must be monitored closely if isolated rash of any severity occurs. Delay in stopping nevirapine treatment after the onset of rash may result in a more serious reaction.

Women appear to be at higher risk than men of developing rash with nevirapine.

In a clinical trial of immediate-release VIRAMUNE, concomitant prednisone use (40 mg per day for the first 14 days of nevirapine administration) was associated with an increase in incidence and severity of rash during the first 6 weeks of nevirapine therapy. Therefore, use of prednisone to prevent nevirapine-associated rash is not recommended.

5.3 Resistance

VIRAMUNE XR must not be used as a single agent to treat HIV-1 or added on as a sole agent to a failing regimen. Resistant virus emerges rapidly when nevirapine is administered as monotherapy. The choice of new antiretroviral agents to be used in combination with nevirapine should take into consideration the potential for cross resistance. When discontinuing an antiretroviral regimen containing VIRAMUNE XR, the long half-life of nevirapine should be taken into account; if antiretrovirals with shorter half-lives than nevirapine are stopped concurrently, low plasma concentrations of nevirapine alone may persist for a week or longer and virus resistance may subsequently develop [see Microbiology(12.4)].

5.4 Drug Interactions

See Table 4 for listings of established and potential drug interactions [see Drug Interactions (7)].

Concomitant use of St. John's wort (Hypericum perforatum) or St. John's wort-containing products and nevirapine is not recommended. Co-administration of St. John's wort with non-nucleoside reverse transcriptase inhibitors (NNRTIs), including nevirapine, is expected to substantially decrease NNRTI concentrations and may result in sub-optimal levels of nevirapine and lead to loss of virologic response and possible resistance to nevirapine or to the class of NNRTIs.

Co-administration of nevirapine and efavirenz is not recommended as this combination has been associated with an increase in adverse reactions and no improvement in efficacy.

5.5 Immune Reconstitution Syndrome

Immune reconstitution syndrome has been reported in patients treated with combination antiretroviral therapy, including nevirapine. During the initial phase of combination antiretroviral treatment, patients whose immune system responds may develop an inflammatory response to indolent or residual opportunistic infections (such as Mycobacterium avium infection, cytomegalovirus, Pneumocystis jiroveci pneumonia, or tuberculosis), which may necessitate further evaluation and treatment.

Autoimmune disorders (such as Graves’ disease, polymyositis, and Guillain-Barré syndrome) have also been reported to occur in the setting of immune reconstitution, however, the time to onset is more variable, and can occur many months after initiation of treatment.

5.6 Fat Redistribution

Redistribution/accumulation of body fat including central obesity, dorsocervical fat enlargement (buffalo hump), peripheral wasting, facial wasting, breast enlargement, and "cushingoid appearance" have been observed in patients receiving antiretroviral therapy. The mechanism and long-term consequences of these events are currently unknown. A causal relationship has not been established.

6 ADVERSE REACTIONS

6.1 Clinical Trial Experience in Adult Patients

Because clinical trials are conducted under widely varying conditions, adverse reaction rates observed in the clinical trials of a drug cannot be directly compared to rates in the clinical trials of another drug and may not reflect the rates observed in clinical practice.

The most serious adverse reactions associated with nevirapine are hepatitis, hepatic failure, Stevens-Johnson syndrome, toxic epidermal necrolysis, and hypersensitivity reactions. Hepatitis/hepatic failure may be isolated or associated with signs of hypersensitivity which may include severe rash or rash accompanied by fever, general malaise, fatigue, muscle or joint aches, blisters, oral lesions, conjunctivitis, facial edema, eosinophilia, granulocytopenia, lymphadenopathy, or renal dysfunction [see Boxed Warning and Warnings and Precautions (5.1, 5.2)].

The most common clinical toxicity of nevirapine is rash, which can be severe or life-threatening [see Boxed Warning and Warnings and Precautions (5.2)]. Rash occurs most frequently within the first 6 weeks of therapy. Rashes are usually mild to moderate, maculopapular erythematous cutaneous eruptions, with or without pruritus, located on the trunk, face and extremities.

The safety database in VIRAMUNE XR clinical trials contains data from 800 subjects treated with VIRAMUNE XR and 654 subjects treated with immediate release VIRAMUNE.

Trial 1100.1486 (VERxVE)

In Trial 1100.1486 (VERxVE) treatment-naïve subjects received a lead-in dose of immediate-release VIRAMUNE 200 mg once daily for 14 days (n=1068) and then were randomized to receive either immediate-release VIRAMUNE 200 mg twice daily (n=506) or VIRAMUNE XR 400 mg once daily (n=505). All subjects received tenofovir + emtricitabine as background therapy. Subjects were enrolled with CD4^+ counts less than 250 cells/mm^3 for women and less than 400 cells/mm^3 for men [see Indications and Usage (1)]. Data on potential symptoms of hepatic events were prospectively collected in this trial. The safety data include all subject visits up to the time of the last subject’s completion of the 96 week endpoint in the trial (mean observation period 98 weeks).

After the lead-in period, the incidence of any hepatic event was 9% in the immediate-release VIRAMUNE group and 6% in the VIRAMUNE XR group; the incidence of symptomatic hepatic events (anorexia, jaundice, vomiting) was 3% and 2%, respectively. The incidence of GRADE 3 or 4 ALT/AST elevation was 8% in both the immediate-release VIRAMUNE group and VIRAMUNE XR group. Overall, there was a comparable incidence of symptomatic hepatic events among men and women enrolled in VERxVE.

Severe or life-threatening rash considered to be related to nevirapine treatment occurred in 1% of subjects during the lead-in phase with immediate-release VIRAMUNE, and in 1% of subjects in either treatment group during the randomization phase. In addition, six cases of Stevens-Johnson syndrome were reported in the trial; all but one occurred within the first 30 days of nevirapine treatment.

No Grade 2 or above adverse reactions judged to be related to treatment by the investigator occurred in more than 2% of subjects during the 14-day lead-in with immediate-release VIRAMUNE (200 mg once daily), with the exception of rash which occurred in 4% of subjects.

Adverse reactions of at least moderate intensity (Grades 2 or above) 2% or more of treatment-naïve subjects receiving either immediate-release VIRAMUNE or VIRAMUNE XR after randomization in Trial 1100.1486 are shown in Table 2.

Table 2 Selected Clinical Adverse Drug Reactions* of at least Moderate Intensity (Grade 2 or above) Occurring in 2% or more of Adult Subjects- Week 96 Analysis of Trial 1100.1486^1
Adverse Drug Reaction | VIRAMUNE Immediate-Release N=506 (%) | VIRAMUNE XR N=505 (%)
Rash^2 | 4 | 5
Diarrhea | 4 | 4
Headache | 4 | 4
Clinical Hepatitis^3 | 4 | 2
Abdominal Pain | 2 | 3
Arthralgia | 2 | 2
Pyrexia | 2 | 1
Nausea | 2 | 1
Fatigue | 2 | 2
* Excludes laboratory abnormalities reported as ADRs
^1 Mean observation period 98 weeks.
^2 Rash includes terms rash, rash maculo-papular, erythema nodosum, rash erythematous, rash papular, skin reaction, Stevens-Johnson syndrome, drug rash with eosinophilia and systemic symptoms (DRESS).
^3 Clinical hepatitis includes terms hepatitis, hepatotoxicity, hepatitis acute, liver disorder, hepatitis toxic, hepatic failure, jaundice.

Laboratory Abnormalities

Liver enzyme test abnormalities (AST, ALT) were observed in subjects receiving VIRAMUNE XR. Asymptomatic elevations in GGT occur frequently but are not a contraindication to continue therapy with nevirapine in the absence of elevations in other liver enzyme tests. Laboratory abnormalities that occurred in trial 1100.1486 are shown in Table 3.

Table 3 Grade 2 to Grade 4 Laboratory Abnormalities that Represent a Worsening from Baseline Observed in at least 5% of Subjects in Either Treatment Group - Trial 1100.1486
Laboratory Parameter (unit) | Limit | VIRAMUNE Immediate-Release (%) (N=506) | VIRAMUNE XR (%) (N=505)
Chemistry
SGPT/ALT (U/L)
Grade 2 | 2.6-5.0 x ULN | 13 | 10
Grade 3 | 5.1-10.0 x ULN | 3 | 4
Grade 4 | >10.0 x ULN | 4 | 2
SGOT/AST (U/L)
Grade 2 | 2.6-5.0 x ULN | 9 | 7
Grade 3 | 5.1-10.0 x ULN | 2 | 3
Grade 4 | >10.0 x ULN | 2 | 2
Amylase (U/L)
Grade 2 | 1.6-2.0 x ULN | 4 | 5
Grade 3 | 2.1-5.0 x ULN | 4 | 2
Grade 4 | >5.0 x ULN | 0 | <1
Phosphate (mg/dL)
Grade 2 | 2.0-2.4 x ULN | 38 | 33
Grade 3 | 1.0-1.9 x ULN | 6 | 7
Grade 4 | <1.0 x ULN | <1 | 0
Hematology
Neutrophils
Grade 2 | 750-999/mm^3 | 7 | 4
Grade 3 | 500-749/mm^3 | 2 | 2
Grade 4 | <500/mm^3 | 1 | 1
Lipids
LDL (mg/dL)
Grade 2 | 160-190 mg/dL | 15 | 15
Grade 3 | >190 mg/dL | 5 | 5
Cholesterol (mg/dL)
Grade 2 | 240-300 mg/dL | 18 | 19
Grade 3 | >300 mg/dL | 4 | 3

Trial 1100.1526 (TRANxITION)

In Trial 1100.1526 (TRANxITION) subjects on immediate-release VIRAMUNE 200 mg twice daily for at least 18 weeks were randomized to either receive VIRAMUNE XR 400 mg once daily (n=295) or remain on their immediate-release VIRAMUNE treatment (n=148). Adverse reactions observed for VIRAMUNE XR subjects (48 week analysis) were similar to those observed in trial 1100.1486, as displayed in Table 1.

6.2 Clinical Trial Experience in Pediatric Patients

Adverse reactions were assessed in Trial 1100.1518, an open-label, multiple-dose, non-randomized, cross-over trial to evaluate the safety and steady-state pharmacokinetic parameters of VIRAMUNE XR tablets in HIV-1-infected pediatric subjects 3 to less than 18 years of age. Safety was further examined in an optional extension phase of the trial. Forty subjects who completed the pharmacokinetic part of the trial were treated with VIRAMUNE XR once daily in combination with other antiretrovirals for a median duration of 33 weeks. The most frequently reported adverse reactions related to VIRAMUNE XR in pediatric subjects were similar to those observed in adults. In pediatric subjects the incidence of Grade 2 or higher drug-related rash was 1%. There were no adverse reactions of Grade 2 or above which were considered to be related to treatment by the investigator that occurred in more than 1% of subjects [see Use in Specific Populations (8.4), Clinical Pharmacology (12.3), and Clinical Studies (14.2)].

6.3 Post-Marketing Experience

The following adverse reactions have been identified during post-approval use of immediate-release VIRAMUNE. Because these reactions are reported voluntarily from a population of uncertain size, it is not always possible to reliably estimate their frequency or establish a causal relationship to drug exposure.

Body as a Whole: fever, somnolence, drug withdrawal [see Drug Interactions (7)], redistribution/accumulation of body fat [see Warnings and Precautions (5.6)]
Gastrointestinal: vomiting
Liver and Biliary: jaundice, fulminant and cholestatic hepatitis, hepatic necrosis, hepatic failure
Hematology: anemia, eosinophilia, neutropenia
Investigations: decreased serum phosphorus
Musculoskeletal: arthralgia, rhabdomyolysis associated with skin and/or liver reactions
Neurologic: paraesthesia
Skin and Appendages: allergic reactions including anaphylaxis, angioedema, bullous eruptions, ulcerative stomatitis and urticaria have all been reported. In addition, hypersensitivity syndrome and hypersensitivity reactions with rash associated with constitutional findings such as fever, blistering, oral lesions, conjunctivitis, facial edema, muscle or joint aches, general malaise, fatigue, or significant hepatic abnormalities [see Warnings and Precautions (5.1)] plus one or more of the following: hepatitis, eosinophilia, granulocytopenia, lymphadenopathy, and/or renal dysfunction have been reported.

7 DRUG INTERACTIONS

Nevirapine is principally metabolized by the liver via the cytochrome P450 isoenzymes, 3A and 2B6. Nevirapine is known to be an inducer of these enzymes. As a result, drugs that are metabolized by these enzyme systems may have lower than expected plasma levels when co-administered with nevirapine.

The results of drug interactions studies with immediate-release VIRAMUNE are expected to also apply to VIRAMUNE XR. The specific pharmacokinetic changes that occur with co-administration of nevirapine and other drugs are listed in Clinical Pharmacology, Table 5. Clinical comments about possible dosage modifications based on established drug interactions are listed in Table 4. The data in Tables 4 and 5 are based on the results of drug interaction studies conducted in HIV-1 seropositive subjects unless otherwise indicated. In addition to established drug interactions, there may be potential pharmacokinetic interactions between nevirapine and other drug classes that are metabolized by the cytochrome P450 system. These potential drug interactions are also listed in Table 4. Although specific drug interaction studies in HIV-1 seropositive subjects have not been conducted for some classes of drugs listed in Table 4, additional clinical monitoring may be warranted when co-administering these drugs.

The in vitro interaction between nevirapine and the antithrombotic agent warfarin is complex. As a result, when giving these drugs concomitantly, plasma warfarin levels may change with the potential for increases in coagulation time. When warfarin is co-administered with nevirapine, anticoagulation levels should be monitored frequently.

Table 4 Established and Potential Drug Interactions: Use With Caution, Alteration in Dose or Regimen May Be Needed Due to Drug Interaction Established Drug Interactions: See Clinical Pharmacology (12.3), Table 5 for Magnitude of Interaction.
Drug Name | Effect on Concentration of Nevirapine or Concomitant Drug | Clinical Comment
HIV Antiviral Agents: Protease Inhibitors (PIs)
Atazanavir/Ritonavir* | ↓ Atazanavir ↑ Nevirapine | Do not co-administer nevirapine with atazanavir because nevirapine substantially decreases atazanavir exposure and there is a potential risk for nevirapine-associated toxicity due to increased nevirapine exposures.
Fosamprenavir* | ↓Amprenavir ↑Nevirapine | Co-administration of nevirapine and fosamprenavir without ritonavir is not recommended.
Fosamprenavir/Ritonavir* | ↓Amprenavir ↑Nevirapine | No dosing adjustments are required when nevirapine is co-administered with 700/100 mg of fosamprenavir/ritonavir twice daily. The combination of nevirapine administered with fosamprenavir/ritonavir once daily has not been studied.
Indinavir* | ↓ Indinavir | The appropriate doses of this combination of indinavir and nevirapine with respect to efficacy and safety have not been established.
Lopinavir/Ritonavir* | ↓Lopinavir | Dosing in adult patients: A dose adjustment of lopinavir/ritonavir to 500/125 mg tablets twice daily or 533/133 mg (6.5 mL) oral solution twice daily is recommended when used in combination with nevirapine. Neither lopinavir/ritonavir tablets nor oral solution should be administered once daily in combination with nevirapine. Dosing in pediatric patients: Please refer to the Kaletra® prescribing information for dosing recommendations based on body surface area and body weight. Neither lopinavir/ritonavir tablets nor oral solution should be administered once daily in combination with nevirapine.
Nelfinavir* | ↓Nelfinavir M8 Metabolite ↓Nelfinavir Cmin | The appropriate doses of the combination of nevirapine and nelfinavir with respect to safety and efficacy have not been established.
Saquinavir/ritonavir | The interaction between nevirapine and saquinavir/ritonavir has not been evaluated | The appropriate doses of the combination of nevirapine and saquinavir/ritonavir with respect to safety and efficacy have not been established.
HIV Antiviral Agents: Non-Nucleoside Reverse Transcriptase Inhibitors (NNRTIs)
Efavirenz* | ↓ Efavirenz | The appropriate doses of these combinations with respect to safety and efficacy have not been established.
Delavirdine Etravirine Rilpivirine | ↓ Efavirenz | Plasma concentrations may be altered. Nevirapine should not be coadministered with another NNRTI as this combination has not been shown to be beneficial.
Other Agents
Analgesics: Methadone* | ↓ Methadone | Methadone levels were decreased; increased dosages may be required to prevent symptoms of opiate withdrawal. Methadone-maintained patients beginning nevirapine therapy should be monitored for evidence of withdrawal and methadone dose should be adjusted accordingly.
Antiarrhythmics: Amiodarone, disopyramide, lidocaine | Plasma concentrations may be decreased. | Appropriate doses for this combination have not been established.
Antibiotics: Clarithromycin* | ↓ Clarithromycin ↑ 14-OH clarithromycin | Clarithromycin exposure was significantly decreased by nevirapine; however, 14-OH metabolite concentrations were increased. Because clarithromycin active metabolite has reduced activity against Mycobacterium avium-intracellulare complex, overall activity against this pathogen may be altered. Alternatives to clarithromycin, such as azithromycin, should be considered.
Rifabutin* | ↑Rifabutin | Rifabutin and its metabolite concentrations were moderately increased. Due to high intersubject variability, however, some patients may experience large increases in rifabutin exposure and may be at higher risk for rifabutin toxicity. Therefore, caution should be used in concomitant administration.
Rifampin* | ↓ Nevirapine | Nevirapine and rifampin should not be administered concomitantly because decreases in nevirapine plasma concentrations may reduce the efficacy of the drug. Physicians needing to treat patients co-infected with tuberculosis and using a nevirapine-containing regimen may use rifabutin instead.
Anticonvulsants: Carbamazepine, clonazepam, ethosuximide | Plasma concentrations of nevirapine and the anticonvulsant may be decreased. | Use with caution and monitor virologic response and levels of anticonvulsants.
Antifungals: Fluconazole* | ↑Nevirapine | Because of the risk of increased exposure to nevirapine, caution should be used in concomitant administration, and patients should be monitored closely for nevirapine-associated adverse events.
Ketoconazole* | ↓ Ketoconazole | Nevirapine and ketoconazole should not be administered concomitantly because decreases in ketoconazole plasma concentrations may reduce the efficacy of the drug.
Itraconazole | ↓ Itraconazole | Nevirapine and itraconazole should not be administered concomitantly due to potential decreases in itraconazole plasma concentrations that may reduce efficacy of the drug.
Antithrombotics: Warfarin | Plasma concentrations may be decreased. | Potential effect on anticoagulation. Monitoring of anticoagulation levels is recommended.
Calcium channel blockers: Diltiazem, nifedipine, verapamil | Plasma concentrations may be decreased. | Appropriate doses for these combinations have not been established.
Cancer chemotherapy: Cyclophosphamide | Plasma concentrations may be increased. | Appropriate doses for this combination have not been established.
Ergot alkaloids: Ergotamine | Plasma concentrations may be decreased. | Appropriate doses for this combination have not been established.
Immunosuppressants: Cyclosporine, tacrolimus, sirolimus | Plasma concentrations may be decreased. | Appropriate doses for these combinations have not been established.
Motility agents: Cisapride | Plasma concentrations may be decreased. | Appropriate doses for this combination have not been established.
Opiate agonists: Fentanyl | Plasma concentrations may be decreased. | Appropriate doses for this combination have not been established.
Oral contraceptives: Ethinyl estradiol and Norethindrone* | ↓ Ethinyl estradiol ↓ Norethindrone | Oral contraceptives and other hormonal methods of birth control should not be used as the sole method of contraception in women taking nevirapine, since nevirapine may lower the plasma levels of these medications. An alternative or additional method of contraception is recommended.
* The interaction between immediate-release VIRAMUNE and the drug was evaluated in a clinical study. The results of drug interaction studies with immediate-release VIRAMUNE are expected to also apply to VIRAMUNE XR.

8 USE IN SPECIFIC POPULATIONS

8.1 Pregnancy

Pregnancy Category B.

There are no adequate and well-controlled trials of nevirapine in pregnant women. The Antiretroviral Pregnancy Registry, which has been surveying pregnancy outcomes since January 1989, has not found an increased risk of birth defects following first trimester exposures to nevirapine. The prevalence of birth defects after any trimester exposure to nevirapine is comparable to the prevalence observed in the general population.

Severe hepatic events, including fatalities, have been reported in pregnant women receiving chronic nevirapine therapy as part of combination treatment of HIV-1 infection. Regardless of pregnancy status, women with CD4^+ cell counts greater than 250 cells/mm^3 should not initiate nevirapine unless the benefit outweighs the risk. It is unclear if pregnancy augments the risk observed in non-pregnant women [see Boxed Warning].

VIRAMUNE XR should be used during pregnancy only if the potential benefit justifies the potential risk to the fetus.

Antiretroviral Pregnancy Registry

To monitor maternal-fetal outcomes of pregnant women exposed to immediate-release VIRAMUNE and VIRAMUNE XR, an Antiretroviral Pregnancy Registry has been established. Physicians are encouraged to register patients by calling (800) 258-4263.

Animal Data

No observable teratogenicity was detected in reproductive studies performed in pregnant rats and rabbits. The maternal and developmental no-observable-effect level dosages produced systemic exposures approximately equivalent to or approximately 50% higher in rats and rabbits, respectively, than those seen at the recommended daily human dose (based on AUC). In rats, decreased fetal body weights were observed due to administration of a maternally toxic dose (exposures approximately 50% higher than that seen at the recommended human clinical dose).

8.3 Nursing Mothers

The Centers for Disease Control and Prevention recommend that HIV-1 infected mothers not breastfeed their infants to avoid risking postnatal transmission of HIV-1. Nevirapine is excreted in breast milk. Because of both the potential for HIV-1 transmission and the potential for serious adverse reactions in nursing infants, mothers should be instructed not to breastfeed if they are receiving VIRAMUNE XR.

8.4 Pediatric Use

VIRAMUNE XR is indicated for use in combination with other antiretroviral agents for the treatment of HIV-1 infection in children 6 to less than 18 years of age [see Indications and Usage (1), Dosage and Administration (2.3)].

The use of VIRAMUNE XR for the treatment of HIV-1 infection in pediatric patients 6 to less than 18 years of age is based on pharmacokinetic, safety, and antiviral activity data from an open-label trial with VIRAMUNE XR. The results of this trial were supported by previous demonstration of efficacy in adult patients [see Adverse Reactions (6.2), Clinical Pharmacology (12.3), and Clinical Studies (14.2)].

VIRAMUNE XR is not recommended for children less than 6 years of age. Trial 1100.1518 did not provide sufficient pharmacokinetic data for children 3 to less than 6 years of age to support the use of VIRAMUNE XR in this age group. Furthermore, VIRAMUNE XR is not recommended for children less than 3 years of age because they are not able to swallow tablets.

8.5 Geriatric Use

Clinical studies of VIRAMUNE XR did not include sufficient numbers of subjects aged 65 and older to determine whether elderly subjects respond differently from younger subjects. In general, dose selection for an elderly patient should be cautious, reflecting the greater frequency of decreased hepatic, renal or cardiac function, and of concomitant disease or other drug therapy.

8.6 Renal Impairment

In subjects with renal impairment (mild, moderate or severe), there were no significant changes in the pharmacokinetics of nevirapine. Nevirapine is extensively metabolized by the liver and nevirapine metabolites are extensively eliminated by the kidney. Nevirapine metabolites may accumulate in patients receiving dialysis; however, the clinical significance of this accumulation is not known. No adjustment in nevirapine dosing is required in patients with CrCL greater than or equal to 20 mL per min. The pharmacokinetics of nevirapine have not been evaluated in patients with CrCl less than 20 mL per min. In patients undergoing chronic hemodialysis, an additional dose of immediate-release VIRAMUNE (200 mg) following each dialysis treatment is indicated [see Dosage and Administration (2.5) and Clinical Pharmacology (12.3)]. VIRAMUNE XR has not been studied in patients with renal dysfunction.

8.7 Hepatic Impairment

Because increased nevirapine levels and nevirapine accumulation may be observed in patients with serious liver disease, do not administer nevirapine to patients with moderate or severe (Child-Pugh Class B or C, respectively) hepatic impairment [see Contraindications (4), Warnings and Precautions (5.1), and Clinical Pharmacology (12.3)]. VIRAMUNE XR has not been evaluated in subjects with hepatic impairment.

10 OVERDOSAGE

There is no known antidote for nevirapine overdosage. Cases of immediate-release VIRAMUNE overdose at doses ranging from 800 to 1800 mg per day for up to 15 days have been reported. Patients have experienced events including edema, erythema nodosum, fatigue, fever, headache, insomnia, nausea, pulmonary infiltrates, rash, vertigo, vomiting and weight decrease. All events subsided following discontinuation of immediate-release VIRAMUNE.

11 DESCRIPTION

VIRAMUNE XR is the brand name for nevirapine extended-release tablets. Nevirapine is a non-nucleoside reverse transcriptase inhibitor (NNRTI) with activity against Human Immunodeficiency Virus Type 1 (HIV-1). Nevirapine is structurally a member of the dipyridodiazepinone chemical class of compounds.

The chemical name of nevirapine is 11-cyclopropyl-5,11-dihydro-4-methyl-6H-dipyrido [3,2-b:2',3'-e][1,4] diazepin-6-one. Nevirapine is a white to off-white crystalline powder with the molecular weight of 266.30 and the molecular formula C15H14N4O. Nevirapine has the following structural formula:

VIRAMUNE XR Tablets are for oral administration. Each tablet contains 100 mg or 400 mg of nevirapine and the inactive ingredients lactose monohydrate, hypromellose, iron oxide, and magnesium stearate.

12 CLINICAL PHARMACOLOGY

12.1 Mechanism of Action

Nevirapine is an antiviral drug [see Microbiology (12.4)].

12.3 Pharmacokinetics

Adults

Absorption and Bioavailability

The single-dose pharmacokinetics of VIRAMUNE XR was studied in 17 healthy volunteers. Nevirapine was absorbed with a median tmax of approximately 24 hrs. The mean Cmax and AUC0-∞ of nevirapine were 2060 ng per mL and 161,000 ng*hr/mL, respectively. The bioavailability of 400 mg of VIRAMUNE XR, relative to 400 mg of immediate-release VIRAMUNE, was approximately 75%.

The multiple-dose pharmacokinetics of VIRAMUNE XR was studied in 24 HIV-1 infected subjects who switched from chronic VIRAMUNE IR to VIRAMUNE XR. The mean nevirapine AUC0-24,ss and Cmin,ss after 19 days of VIRAMUNE XR dosing under fasted conditions were 82,000 ng*hr/mL and 2920 ng per mL, respectively. When VIRAMUNE XR was administered under fed conditions, the mean nevirapine AUC0-24,ss and Cmin,ss were 96,700 ng*hr/mL and 3150 ng per mL, respectively. The bioavailability of 400 mg of VIRAMUNE XR, relative to 400 mg of immediate-release VIRAMUNE, under fasted and fed conditions, was 80% and 94%, respectively. The difference in the bioavailability of nevirapine, when VIRAMUNE XR is dosed under fasted or fed conditions, is not considered clinically relevant. VIRAMUNE XR can be taken with or without food.

In single-dose, parallel-group bioavailability trial (1100.1517) in adults, the VIRAMUNE XR 100 mg tablet exhibited extended-release characteristics of prolonged absorption and lower maximal concentration, as compared to the immediate-release VIRAMUNE 200 mg tablet.

Distribution

Nevirapine is highly lipophilic and is essentially nonionized at physiologic pH. Following intravenous administration to healthy adults, the apparent volume of distribution (Vdss) of nevirapine was 1.21 ± 0.09 L/kg, suggesting that nevirapine is widely distributed in humans. Nevirapine readily crosses the placenta and is also found in breast milk [see Use In Specific Populations (8.3)]. Nevirapine is about 60% bound to plasma proteins in the plasma concentration range of 1-10 mcg per mL. Nevirapine concentrations in human cerebrospinal fluid (n=6) were 45% (±5%) of the concentrations in plasma; this ratio is approximately equal to the fraction not bound to plasma protein.

Metabolism/Elimination

In vivo studies in humans and in vitro studies with human liver microsomes have shown that nevirapine is extensively biotransformed via cytochrome P450 (oxidative) metabolism to several hydroxylated metabolites. In vitro studies with human liver microsomes suggest that oxidative metabolism of nevirapine is mediated primarily by cytochrome P450 (CYP) isozymes from the CYP3A and CYP2B6 families, although other isozymes may have a secondary role. In a mass balance/excretion trial in eight healthy male volunteers dosed to steady state with immediate-release VIRAMUNE 200 mg given twice daily followed by a single 50 mg dose of ^14C-nevirapine, approximately 91.4 ± 10.5% of the radiolabeled dose was recovered, with urine (81.3 ± 11.1%) representing the primary route of excretion compared to feces (10.1 ± 1.5%). Greater than 80% of the radioactivity in urine was made up of glucuronide conjugates of hydroxylated metabolites. Thus cytochrome P450 metabolism, glucuronide conjugation, and urinary excretion of glucuronidated metabolites represent the primary route of nevirapine biotransformation and elimination in humans. Only a small fraction (less than 5%) of the radioactivity in urine (representing less than 3% of the total dose) was made up of parent compound; therefore, renal excretion plays a minor role in elimination of the parent compound.

Nevirapine is an inducer of hepatic cytochrome P450 (CYP) metabolic enzymes 3A and 2B6. Nevirapine induces CYP3A and CYP2B6 by approximately 20-25%, as indicated by erythromycin breath test results and urine metabolites. Autoinduction of CYP3A and CYP2B6 mediated metabolism leads to an approximately 1.5- to 2-fold increase in the apparent oral clearance of nevirapine as treatment continues from a single dose to two-to-four weeks of dosing with 200-400 mg per day of immediate-release VIRAMUNE. Autoinduction also results in a corresponding decrease in the terminal phase half-life of nevirapine in plasma, from approximately 45 hours (single dose) to approximately 25-30 hours following multiple dosing with 200-400 mg per day.

Specific Populations

Renal Impairment

HIV-1 seronegative adults with mild (CrCL 50-79 mL per min; n=7), moderate (CrCL 30-49 mL per min; n=6), or severe (CrCL less than 30 mL per min; n=4) renal impairment received a single 200 mg dose of immediate-release VIRAMUNE in a pharmacokinetic trial. These subjects did not require dialysis. The trial included six additional subjects with renal failure requiring dialysis.

In subjects with renal impairment (mild, moderate or severe), there were no significant changes in the pharmacokinetics of nevirapine. However, subjects requiring dialysis exhibited a 44% reduction in nevirapine AUC over a one-week exposure period. There was also evidence of accumulation of nevirapine hydroxy-metabolites in plasma in subjects requiring dialysis. An additional 200 mg dose of immediate-release VIRAMUNE following each dialysis treatment is indicated [see Dosage and Administration (2.5) and Use in Specific Populations (8.6)]. VIRAMUNE XR has not been studied in patients with renal dysfunction.

Hepatic Impairment

In a steady-state trial comparing 46 subjects with mild (n=17; expansion of some portal areas; Ishak Score 1-2), moderate (n=20; expansion of most portal areas with occasional portal-to-portal and portal-to-central bridging; Ishak Score 3-4), or severe (n=9; marked bridging with occasional cirrhosis without decompensation indicating Child-Pugh A; Ishak Score 5-6) fibrosis as a measure of hepatic impairment, the multiple dose pharmacokinetic disposition of nevirapine and its five oxidative metabolites were not altered. However, approximately 15% of these subjects with hepatic fibrosis had nevirapine trough concentrations above 9,000 mcg per mL (2-fold the usual mean trough). Therefore, patients with hepatic impairment should be monitored carefully for evidence of drug-induced toxicity [see Warnings and Precautions (5.1)]. The subjects studied were receiving antiretroviral therapy containing immediate-release VIRAMUNE 200 mg twice daily for at least 6 weeks prior to pharmacokinetic sampling, with a median duration of therapy of 3.4 years.

In a pharmacokinetic trial where HIV-1 negative cirrhotic subjects with mild (Child-Pugh A; n=6) or moderate (Child-Pugh B; n=4) hepatic impairment received a single 200 mg dose of immediate-release VIRAMUNE, a significant increase in the AUC of nevirapine was observed in one subject with Child-Pugh B and ascites suggesting that patients with worsening hepatic function and ascites may be at risk of accumulating nevirapine in the systemic circulation. Because nevirapine induces its own metabolism with multiple dosing, this single-dose trial may not reflect the impact of hepatic impairment on multiple-dose pharmacokinetics.

Do not administer nevirapine to patients with moderate or severe (Child-Pugh Class B or C, respectively) hepatic impairment [see Contraindications (4), Warnings and Precautions (5.1), and Use in Specific Populations (8.7)]. VIRAMUNE XR has not been evaluated in patients with hepatic impairment.

Gender

In the multinational 2NN trial of immediate-release VIRAMUNE, a population pharmacokinetic substudy of 1077 subjects was performed that included 391 females. Female subjects showed a 13.8% lower clearance of nevirapine than did men. Since neither body weight nor Body Mass Index (BMI) had an influence on the clearance of nevirapine, the effect of gender cannot solely be explained by body size.

The effects of gender on the pharmacokinetics of VIRAMUNE XR have been investigated in Trial 1100.1486. Female subjects tend to have higher (approximately 20 - 30%) trough concentrations in both VIRAMUNE XR and immediate-release VIRAMUNE treatment groups.

Race

An evaluation of nevirapine plasma concentrations (pooled data from several clinical trials) from HIV-1-infected subjects (27 Black, 24 Hispanic, 189 Caucasian) revealed no marked difference in nevirapine steady-state trough concentrations (median Cminss = 4.7 mcg per mL Black, 3.8 mcg per mL Hispanic, 4.3 mcg per mL Caucasian) with long-term treatment with immediate-release VIRAMUNE at 400 mg per day. However, the pharmacokinetics of nevirapine have not been evaluated specifically for the effects of ethnicity.

Black subjects (n=80/group) in Trial 1100.1486 showed approximately 30 to 35% higher trough concentrations than Caucasian subjects (250-325 subjects/group) in both immediate-release VIRAMUNE and VIRAMUNE XR treatment groups over 96 weeks of treatment at 400 mg per day.

Geriatric Patients

Nevirapine pharmacokinetics in HIV-1-infected adults do not appear to change with age (range 18–68 years); however, nevirapine has not been extensively evaluated in patients beyond the age of 65 years [see Use in Specific Populations (8.5)].

Pediatric Patients

The pharmacokinetics of VIRAMUNE XR were assessed in HIV-1 infected children 3 to less than 18 years of age. Children enrolled received weight or body surface area dose-adjusted immediate-release VIRAMUNE in combination with other antiretrovirals for a minimum of 18 weeks and then were switched to VIRAMUNE XR tablets in combination with other antiretrovirals for 10 days, after which steady-state pharmacokinetic parameters were determined.

Overall, the mean systemic nevirapine exposures in children 6 to less than 18 years of age following administration of VIRAMUNE XR and immediate-release VIRAMUNE were similar. Based on intensive PK data (N=17), the observed geometric mean ratios of VIRAMUNE XR to immediate-release VIRAMUNE were approximately 97% for Cmin,ss and 94% for AUCss with 90% confidence intervals within 80% - 125%; the ratio for Cmax,ss was lower and consistent with a once daily extended-release dosage form.

Trial 1100.1518 did not provide sufficient pharmacokinetic data for children 3 to less than 6 years of age to support the use of VIRAMUNE XR in this age group.

Drug Interactions [see Drug Interactions (7)]

Nevirapine induces hepatic cytochrome P450 metabolic isoenzymes 3A and 2B6. Co-administration of VIRAMUNE XR and drugs primarily metabolized by CYP3A or CYP2B6 may result in decreased plasma concentrations of these drugs and attenuate their therapeutic effects.

While primarily an inducer of cytochrome P450 3A and 2B6 enzymes, nevirapine may also inhibit this system. Among human hepatic cytochrome P450s, nevirapine was capable in vitro of inhibiting the 10-hydroxylation of (R)-warfarin (CYP3A). The estimated Ki for the inhibition of CYP3A was 270 micromolar, a concentration that is unlikely to be achieved in patients as the therapeutic range is less than 25 micromolar. Therefore, nevirapine may have minimal inhibitory effect on other substrates of CYP3A.

Nevirapine does not appear to affect the plasma concentrations of drugs that are substrates of other CYP450 enzyme systems, such as 1A2, 2D6, 2A6, 2E1, 2C9, or 2C19.

Table 5 (see below) contains the results of drug interaction trials performed with immediate-release VIRAMUNE and other drugs likely to be co-administered. The effects of nevirapine on the AUC, Cmax, and Cmin of co-administered drugs are summarized. Results of drug interaction studies with immediate-release VIRAMUNE are expected to also apply to VIRAMUNE XR.

Table 5 Drug Interactions: Changes in Pharmacokinetic Parameters for Co-administered Drug in the Presence of Immediate-Release VIRAMUNE (All interaction studies were conducted in HIV-1 positive subjects)
Co-administered Drug | Dose of Co-administered Drug | Dose Regimen of immediate-release VIRAMUNE | n | % Change of Co-administered Drug Pharmacokinetic Parameters (90% CI)
Antiretrovirals |  |  |  | AUC | Cmax | Cmin
Atazanavir/Ritonavira, d | 300/100 mg QD day 4–13, then 400/100 mg QD, day 14–23 | 200 mg BID day 1-23. Subjects were treated with nevirapine prior to trial entry. | 23 | Atazanavir 300/100 mg ↓42 (↓52 to ↓29) | Atazanavir 300/100 mg ↓28 (↓40 to ↓14) | Atazanavir 300/100 mg ↓72 (↓80 to ↓60)
Atazanavir/Ritonavira, d | 300/100 mg QD day 4–13, then 400/100 mg QD, day 14–23 | 200 mg BID day 1-23. Subjects were treated with nevirapine prior to trial entry. | 23 | Atazanavir 400/100 mg ↓19 (↓35 to ↑2) | Atazanavir 400/100 mg ↑2 (↓15 to ↑24) | Atazanavir 400/100 mg ↓59 (↓73 to ↓40)
Darunavir/Ritonavir e | 400/100 mg BID | 200 mg BID | 8 | ↑24 (↓3 to ↑57) | ↑40 (↑14 to ↑73) | ↑2 (↓21 to ↑32)
Didanosine | 100-150 mg BID | 200 mg QD x 14 days; 200 mg BID x 14 days | 18 | ⇔ | ⇔ | §
Efavirenza | 600 mg QD | 200 mg QD x 14 days; 400 mg QD x 14 days | 17 | ↓28 (↓34 to ↓14) | ↓12 (↓23 to ↑1) | ↓32 (↓35 to ↓19)
Fosamprenavir | 1400 mg BID | 200 mg BID. Subjects were treated with nevirapine prior to trial entry. | 17 | ↓33 (↓45 to ↓20) | ↓25 (↓37 to ↓10) | ↓35 (↓50 to ↓15)
Fosamprenavir/Ritonavir | 700/100 mg BID | 200 mg BID. Subjects were treated with nevirapine prior to trial entry | 17 | ↓11 (↓23 to ↑3) | ⇔ | ↓19 (↓32 to ↓4)
Indinavira | 800 mg q8H | 200 mg QD x 14 days; 200 mg BID x 14 days | 19 | ↓31 (↓39 to ↓22) | ↓15 (↓24 to ↓4) | ↓44 (↓53 to ↓33)
Lopinavira, b | 300/75 mg/m^2 (lopinavir/ ritonavir) b | 7 mg/kg or 4 mg/kg QD x 2 weeks; BID x 1 week | 12, 15 c | ↓22 (↓44 to ↑9) | ↓14 (↓36 to ↑16) | ↓55 (↓75 to ↓19)
Lopinavira | 400/100 mg BID (lopinavir/ritonavir) | 200 mg QD x 14 days; 200 mg BID >1 year | 22, 19 c | ↓27 (↓47 to ↓2) | ↓19 (↓38 to ↑5) | ↓51 (↓72 to ↓26)
Maraviroc f | 300 mg SD | 200 mg BID | 8 | ↑1 (↓35 to ↑55) | ↑54 (↓6 to ↑151) | ⇔
Nelfinavira | 750 mg TID | 200 mg QD x 14 days; 200 mg BID x 14 days | 23 | ⇔ | ⇔ | ↓32 (↓50 to ↑5)
Nelfinavir-M8 metabolite |  |  |  | ↓62 (↓70 to ↓53) | ↓59 (↓68 to ↓48) | ↓66 (↓74 to ↓55)
Ritonavir | 600 mg BID | 200 mg QD x 14 days; 200 mg BID x 14 days | 18 | ⇔ | ⇔ | ⇔
Stavudine | 30-40 mg BID | 200 mg QD x 14 days; 200 mg BID x 14 days | 22 | ⇔ | ⇔ | §
Zalcitabine | 0.125-0.25 mg TID | 200 mg QD x 14 days; 200 mg BID x 14 days | 6 | ⇔ | ⇔ | §
Zidovudine | 100-200 mg TID | 200 mg QD x 14 days; 200 mg BID x 14 days | 11 | ↓28 (↓40 to ↓4) | ↓30 (↓51 to ↑14) | §
Other Medications |  |  |  | AUC | Cmax | Cmin
Clarithromycina | 500 mg BID | 200 mg QD x 14 days; 200 mg BID x 14 days | 15 | ↓31 (↓38 to ↓24) | ↓23 (↓31 to ↓14) | ↓56 (↓70 to ↓36)
Metabolite 14-OH-clarithromycin |  |  |  | ↑42 (↑16 to ↑73) | ↑47 (↑21 to ↑80) | ⇔
Ethinyl estradiola and Norethindronea | 0.035 mg (as Ortho-Novum® 1/35) | 200 mg QD x 14 days; 200 mg BID x 14 days | 10 | ↓20 (↓33 to ↓3) | ⇔ | §
Ethinyl estradiola and Norethindronea | 1 mg (as Ortho-Novum® 1/35) | 200 mg QD x 14 days; 200 mg BID x 14 days | 10 | ↓19 (↓30 to ↓7) | ↓16 (↓27 to ↓3) | §
Depomedroxy-progesterone acetate | 150 mg every 3 months | 200 mg QD x 14 days; 200 mg BID x 14 days | 32 | ⇔ | ⇔ | ⇔
Fluconazole | 200 mg QD | 200 mg QD x 14 days; 200 mg BID x 14 days | 19 | ⇔ | ⇔ | ⇔
Ketoconazolea | 400 mg QD | 200 mg QD x 14 days; 200 mg BID x 14 days | 21 | ↓72 (↓80 to ↓60) | ↓44 (↓58 to ↓27) | §
Methadonea | Individual Subject Dosing | 200 mg QD x 14 days; 200 mg BID ≥7 days | 9 | In a controlled pharmacokinetic trial with 9 subjects receiving chronic methadone to whom steady-state nevirapine therapy was added, the clearance of methadone was increased by 3-fold, resulting in symptoms of withdrawal, requiring dose adjustments in 10 mg segments, in 7 of the 9 subjects. Methadone did not have any effect on nevirapine clearance.
Rifabutina | 150 or 300 mg QD | 200 mg QD x 14 days; 200 mg BID x 14 days | 19 | ↑17 (↓2 to ↑40) | ↑28 (↑9 to ↑51) | ⇔
Metabolite 25-O-desacetyl-rifabutin |  |  |  | ↑24 (↓16 to ↑84) | ↑29 (↓2 to ↑68) | ↑22 (↓14 to ↑74)
Rifampina | 600 mg QD | 200 mg QD x 14 days; 200 mg BID x 14 days | 14 | ↑11 (↓4 to ↑28) | ⇔ | §
§ = Cmin below detectable level of the assay
↑ = Increase, ↓ = Decrease, ⇔ = No Effect
a For information regarding clinical recommendations, see Drug Interactions (7).
b Pediatric subjects ranging in age from 6 months to 12 years
c Parallel group design; n for VIRAMUNE+lopinavir/ritonavir, n for lopinavir/ritonavir alone.
d Parallel group design; n=23 for atazanavir/ritonavir + nevirapine, n=22 for atazanavir/ritonavir without nevirapine. Changes in atazanavir PK are relative to atazanavir/ritonavir 300/100 mg alone.
e Based on between-trial comparison.
f Based on historical controls.

Because of the design of the drug interaction trials (addition of 28 days of VIRAMUNE therapy to existing HIV-1 therapy), the effect of the concomitant drug on plasma nevirapine steady-state concentrations was estimated by comparison to historical controls.

Administration of rifampin had a clinically significant effect on nevirapine pharmacokinetics, decreasing AUC and Cmax by greater than 50%. Administration of fluconazole resulted in an approximate 100% increase in nevirapine exposure, based on a comparison to historic data [see Drug Interactions (7)]. The effect of other drugs listed in Table 5 on nevirapine pharmacokinetics was not significant. No significant interaction was observed when tipranavir was co-administered with low-dose ritonavir and nevirapine.

12.4 Microbiology

Mechanism of Action

Nevirapine is a non-nucleoside reverse transcriptase inhibitor (NNRTI) of HIV-1. Nevirapine binds directly to reverse transcriptase (RT) and blocks the RNA-dependent and DNA-dependent DNA polymerase activities by causing a disruption of the enzyme's catalytic site. The activity of nevirapine does not compete with template or nucleoside triphosphates. HIV-2 RT and eukaryotic DNA polymerases (such as human DNA polymerases α, β, γ, or δ) are not inhibited by nevirapine.

Antiviral Activity

The antiviral activity of nevirapine has been measured in a variety of cell lines including peripheral blood mononuclear cells, monocyte-derived macrophages, and lymphoblastoid cell lines. In an assay using human embryonic kidney 293 cells, the median EC50 value (50% inhibitory concentration) of nevirapine was 90 nM against a panel of 2923 wild-type isolates of HIV-1 that were primarily (93%) clade B clinical isolates from the United States. The 99th percentile EC50 value was 470 nM in this trial. The median EC50 value was 63 nM (range 14-302 nM, n=29) against clinical isolates of HIV-1 clades A, B, C, D, F, G, and H, and circulating recombinant forms CRF01_AE, CRF02_AG and CRF12_BF. Nevirapine had no antiviral activity in cell culture against group O HIV-1 isolates (n=3) or HIV-2 isolates (n=3) replicating in cord blood mononuclear cells. Nevirapine in combination with efavirenz exhibited strong antagonistic anti-HIV-1 activity in cell culture and was additive to antagonistic with the protease inhibitor ritonavir or the fusion inhibitor enfuvirtide. Nevirapine exhibited additive to synergistic anti-HIV-1 activity in combination with the protease inhibitors amprenavir, atazanavir, indinavir, lopinavir, nelfinavir, saquinavir and tipranavir, and the NRTIs abacavir, didanosine, emtricitabine, lamivudine, stavudine, tenofovir and zidovudine. The anti-HIV-1 activity of nevirapine was antagonized by the anti-HBV drug adefovir and by the anti-HCV drug ribavirin in cell culture.

Resistance

HIV-1 isolates with reduced susceptibility (100- to 250-fold) to nevirapine emerge in cell culture. Genotypic analysis showed mutations in the HIV-1 RT gene encoding Y181C and/or V106A substitutions depending upon the virus strain and cell line employed. Time to emergence of nevirapine resistance in cell culture was not altered when selection included nevirapine in combination with several other NNRTIs.

Phenotypic and genotypic changes in HIV-1 isolates from treatment-naïve subjects receiving either nevirapine (n=24) or nevirapine and zidovudine (n=14) were monitored in Phase 1 and 2 trials ranging from 1 to 12 weeks or longer. After 1 week of nevirapine monotherapy, isolates from 3/3 subjects had decreased susceptibility to nevirapine in cell culture. One or more of the RT mutations resulting in amino acid substitutions K103N, V106A, V108I, Y181C, Y188C, and G190A were detected in HIV-1 isolates from some subjects as early as 2 weeks after therapy initiation. By week eight of nevirapine monotherapy, 100% of the subjects tested (n=24) had HIV-1 isolates with a greater than 100-fold decrease in susceptibility to nevirapine in cell culture compared to baseline, and had one or more of the nevirapine-associated RT resistance substitutions. Nineteen of these subjects (80%) had isolates with Y181C substitutions regardless of dose.

Genotypic analysis of isolates from antiretroviral-naïve subjects experiencing virologic failure (n=71) receiving nevirapine once daily (n=25) or twice daily (n=46) in combination with lamivudine and stavudine (trial 2NN) for 48 weeks showed that isolates from 8/25 and 23/46 subjects, respectively, contained one or more of the following NNRTI resistance-associated substitutions: Y181C, K101E, G190A/S, K103N, V106A/M, V108I, Y188C/L, A98G, F227L, and M230L.

For trial 1100.1486, genotypic analysis was performed for baseline and on-therapy isolates from 23 and 34 subjects who experienced virologic failure in the VIRAMUNE XR and immediate-release VIRAMUNE treatment group, respectively. Nevirapine resistance-associated substitutions developed in the on-therapy isolates of 78% (18/23) of the subjects who had virologic failures in the VIRAMUNE XR treatment group and 88% (30/34) of the subjects in the immediate-release VIRAMUNE treatment group, respectively. The Y181C nevirapine resistance-associated substitution was found alone or in combination with other nevirapine resistance-associated substitutions (K101E, K103N, V106A, V108I, V179D/E/I, Y188 C/F/H/L/N, G190A, P225H, F227L, M230L) in isolates from 14 subjects failing VIRAMUNE XR treatment and 25 subjects failing immediate-release VIRAMUNE treatment. On-therapy isolates from 1 subject in VIRAMUNE XR treatment group developed a novel amino acid substitution Y181I and isolates from another subject in the immediate-release VIRAMUNE treatment group developed a novel amino acid substitution Y188N. Phenotypic analysis showed that Y188N and Y181I substitutions conferred 103- and 22-fold reductions in susceptibility to nevirapine, respectively.

Cross-resistance

Rapid emergence of HIV-1 strains which are cross-resistant to NNRTIs has been observed in cell culture. Nevirapine-resistant HIV-1 isolates were cross-resistant to the NNRTIs delavirdine, efavirenz, and etravirine. The Y188N conferred 22- and 7-fold reductions in susceptibility to delavirdine and efavirenz, respectively, but showed no decrease in susceptibility to etravirine. Similarly, the Y181I substitution reduced susceptibility to delavirdine and etravirine 3- and 8-fold, respectively, but did not reduce susceptibility to efavirenz. However, nevirapine-resistant isolates were susceptible to the NRTIs ddI and ZDV. Similarly, ZDV-resistant isolates were susceptible to nevirapine in cell culture.

13 NONCLINICAL TOXICOLOGY

13.1 Carcinogenesis, Mutagenesis, Impairment of Fertility

Carcinogenesis
Long-term carcinogenicity studies in mice and rats were carried out with nevirapine. Mice were dosed with 0, 50, 375 or 750 mg/kg/day for two years. Hepatocellular adenomas and carcinomas were increased at all doses in males and at the two high doses in females. In studies in which rats were administered nevirapine at doses of 0, 3.5, 17.5 or 35 mg/kg/day for two years, an increase in hepatocellular adenomas was seen in males at all doses and in females at the high dose. The systemic exposure (based on AUCs) at all doses in the two animal studies was lower than that measured in humans at the 200 mg twice daily dose of immediate-release VIRAMUNE. The mechanism of the carcinogenic potential is unknown. However, in genetic toxicology assays, nevirapine showed no evidence of mutagenic or clastogenic activity in a battery of in vitro and in vivo studies. These included microbial assays for gene mutation (Ames: Salmonella strains and E. coli), mammalian cell gene mutation assay (CHO/HGPRT), cytogenetic assays using a Chinese hamster ovary cell line and a mouse bone marrow micronucleus assay following oral administration. Given the lack of genotoxic activity of nevirapine, the relevance to humans of hepatocellular neoplasms in nevirapine-treated mice and rats is not known. In reproductive toxicology studies, evidence of impaired fertility was seen in female rats at doses providing systemic exposure, based on AUC, approximately equivalent to that provided with the recommended clinical dose.

Mutagenesis
However, in genetic toxicology assays, nevirapine showed no evidence of mutagenic or clastogenic activity in a battery of in vitro and in vivo studies. These included microbial assays for gene mutation (Ames: Salmonella strains and E. coli), mammalian cell gene mutation assay (CHO/HGPRT), cytogenetic assays using a Chinese hamster ovary cell line and a mouse bone marrow micronucleus assay following oral administration. Given the lack of genotoxic activity of nevirapine, the relevance to humans of hepatocellular neoplasms in nevirapine-treated mice and rats is not known.

Impairment of Fertility
In reproductive toxicology studies, evidence of impaired fertility was seen in female rats at doses providing systemic exposure, based on AUC, approximately equivalent to that provided with the recommended clinical dose.

13.2 Animal Toxicology and/or Pharmacology

Animal studies have shown that nevirapine is widely distributed to nearly all tissues and readily crosses the blood-brain barrier.

14 CLINICAL STUDIES

14.1 Adult Patients

The clinical efficacy of VIRAMUNE XR is based on 96-week data from an ongoing, randomized, double-blind, double-dummy Phase 3 trial (Trial 1100.1486, VERxVE) in treatment-naïve subjects and on 48-week data in an ongoing, randomized, open-label trial in subjects who switched from immediate-release VIRAMUNE tablets administered twice daily to VIRAMUNE XR tablets administered once daily (Trial 1100.1526, TRANxITION).

Treatment-naïve Subjects

Trial 1100.1486 (VERxVE) is a Phase 3 trial in which treatment-naïve subjects received immediate-release VIRAMUNE 200 mg once daily for 14 days and then were randomized to receive either immediate-release VIRAMUNE 200 mg twice daily or VIRAMUNE XR 400 mg once daily. All subjects received tenofovir + emtricitabine as background therapy. Randomization was stratified by screening HIV-1 RNA level (less than or equal to 100,000 copies per mL and greater than 100,000 copies per mL). Subject demographic and baseline disease characteristics were balanced between the two treatment groups. With respect to demographics: 85% of the subjects were male, 75% were white, 20% were black, and approximately 29% were from North America. With respect to baseline disease characteristics: mean viral load was 4.7 log10 copies per mL, mean CD4^+ cell count was 228 cells/mm^3 and 73% of subjects had clade B HIV-1 subtype. Approximately two-thirds of the subjects had a baseline HIV-RNA level of less than or equal to 100,000 copies per mL.

Table 6 describes week 96 outcomes in the Trial 1100.1486 (VERxVE). These outcomes include all subjects who were randomized after the 14 day lead-in with immediate-release VIRAMUNE and received at least one dose of blinded study medication.

Table 6 Outcomes at Week 96 in Trial 1100.1486
 | Week 96
 | VIRAMUNE Immediate-Release N=506 | VIRAMUNE XR N=505
Virologic Success - HIV RNA < 50 copies/mL | 67% | 69%
Virologic Failure # | 18% | 17%
No Virologic Data at Week 96 Window Reasons Discontinued trial/study drug due to adverse event or death* Discontinued trial/study drug for other reasons** Missing data during window but on trial | 10% 5% <1% | 8% 5% 1%
#Includes subjects who changed optimized background therapy (OBT) to new class or changed OBT not permitted per protocol or due to lack of efficacy prior to Week 96, subjects who discontinued prior to Week 96 for lack or loss of efficacy and subjects with HIV RNA greater than or equal to 50 copies/mL in the Week 96 window.
*Includes subjects who discontinued due to adverse events or death at any time point from Day 1 through the Week 96 window if this resulted in no virologic data on treatment during the specified window.
**Other includes: withdrew consent, lost to follow-up, moved away, etc.

At 96 weeks, mean change from baseline in CD4^+ cell count adjusting for baseline HIV-1 viral load stratum was 222 cells/mm^3 and 244 cells/mm^3 for the groups receiving immediate-release VIRAMUNE and VIRAMUNE XR, respectively.

Subjects Switching from Immediate-release VIRAMUNE to VIRAMUNE XR

Trial 1100.1526 (TRANxITION) is a Phase 3 trial to evaluate safety and antiviral activity of switching from immediate-release VIRAMUNE to VIRAMUNE XR. In this open-label trial, 443 subjects already on an antiviral regimen containing immediate-release VIRAMUNE 200 mg twice daily with HIV-1 RNA less than 50 copies per mL were randomized in a 2:1 ratio to VIRAMUNE XR 400 mg once daily or immediate-release VIRAMUNE 200 mg twice daily. Approximately half of the subjects had tenofovir+emtricitabine as their background therapy, with the remaining subjects receiving abacavir sulfate+lamivudine or zidovudine+lamivudine. Approximately half of the subjects had at least 3 years of exposure to immediate-release VIRAMUNE prior to entering the trial.

At 48 weeks after randomization in Trial 1100.1526, 91% of subjects receiving immediate-release VIRAMUNE 200 mg twice daily and 93% of subjects receiving VIRAMUNE XR 400 mg once daily continued to have HIV-1 RNA less than 50 copies per mL.

14.2 Pediatric Patients

Trial 1100.1518 was an open-label, multiple-dose, non-randomized, crossover trial performed in 85 HIV-1 infected pediatric subjects 3 to less than 18 years of age who had received at least 18 weeks of immediate-release VIRAMUNE and had plasma HIV-1 RNA less than 50 copies per mL prior to trial enrollment. Subjects were stratified according to age (3 to less than 6 years, 6 to less than 12 years, and 12 to less than 18 years). Following a 10-day period with immediate-release VIRAMUNE, subjects were treated with VIRAMUNE XR tablets once daily in combination with other antiretrovirals for 10 days, after which steady-state pharmacokinetic parameters were determined. Forty of the 80 subjects who completed the initial part of the study were enrolled in an optional extension phase of the trial which evaluated the safety and antiviral activity of VIRAMUNE XR through a minimum of 24 weeks of treatment. Zidovudine or stavudine plus lamivudine were the most commonly used background therapies in subjects who entered the optional extension phase.

Baseline demographics included: 55% of the subjects were female, 93% were black, 7% were white, and approximately 84% were from Africa. Subjects had a median baseline CD4^+ cell count of 925 cells/mm^3 (range 207 to 2057 cells/mm^3).

Of the 40 subjects who entered the treatment extension phase, 39 completed at least 24 weeks of treatment and one subject discontinued prematurely due to an adverse reaction. After 24 weeks or more of treatment with VIRAMUNE XR, all 39 subjects continued to have plasma HIV-1 RNA less than 50 copies per mL. Median CD4^+ cell counts for the 3 to less than 6 year, 6 to less than 12 year, and 12 to less than 18 year age groups were 1113 cells/mm^3, 853 cells/mm^3, and 682 cells/mm^3, respectively. These CD4^+ cell counts were similar to those observed at baseline.

16 HOW SUPPLIED/STORAGE AND HANDLING

VIRAMUNE XR tablets, 400 mg, are yellow, oval, biconvex tablets, debossed with "V04" on one side and the Boehringer Ingelheim logo on the other side.

VIRAMUNE XR 400 mg tablets are supplied in bottles of 30 (NDC 54868-6370-0).

Storage

Store at 25°C (77°F); excursions permitted to 15°C–30°C (59°F–86°F) [see USP Controlled Room Temperature]. Store in a safe place out of the reach of children.

17 PATIENT COUNSELING INFORMATION

See FDA-approved patient labeling (Medication Guide).

17.1 Hepatotoxicity and Skin Reactions

Inform patients of the possibility of severe liver disease or skin reactions associated with nevirapine that may result in death. Instruct patients developing signs or symptoms of liver disease or severe skin reactions to discontinue nevirapine and seek medical attention immediately, including performance of laboratory monitoring. Symptoms of liver disease include fatigue, malaise, anorexia, nausea, jaundice, acholic stools, liver tenderness or hepatomegaly. Symptoms of severe skin or hypersensitivity reactions include rash accompanied by fever, general malaise, fatigue, muscle or joint aches, blisters, oral lesions, conjunctivitis, facial edema, and/or hepatitis.

Intensive clinical and laboratory monitoring, including liver enzymes, is essential during the first 18 weeks of therapy with nevirapine to detect potentially life-threatening hepatotoxicity and skin reactions. However, liver disease can occur after this period; therefore, monitoring should continue at frequent intervals throughout nevirapine treatment. Extra vigilance is warranted during the first 6 weeks of therapy, which is the period of greatest risk of hepatic events and skin reactions. Advise patients with signs and symptoms of hepatitis to discontinue nevirapine and seek medical evaluation immediately. If nevirapine is discontinued due to hepatotoxicity, do not restart it. Patients, particularly women, with increased CD4^+ cell count at initiation of nevirapine therapy (greater than 250 cells/mm^3 in women and greater than 400 cells/mm^3 in men) are at substantially higher risk for development of symptomatic hepatic events, often associated with rash. Advise patients that co-infection with hepatitis B or C and/or increased transaminases at the start of therapy with nevirapine are associated with a greater risk of later symptomatic events (6 weeks or more after starting nevirapine) and asymptomatic increases in AST or ALT [see Boxed Warning and Warnings and Precautions (5.1)].

The majority of rashes associated with nevirapine occur within the first 6 weeks of initiation of therapy. Instruct patients that if any rash occurs during the two-week lead-in period with immediate-release VIRAMUNE, do not initiate VIRAMUNE XR until the rash resolves. The total duration of the lead-in dosing period with immediate-release VIRAMUNE should not exceed 28 days, at which point an alternative regimen may need to be started. Any patient experiencing a rash should have their liver enzymes (AST, ALT) evaluated immediately. Patients with severe rash or hypersensitivity reactions should discontinue nevirapine immediately and consult a physician. Nevirapine should not be restarted following severe skin rash or hypersensitivity reaction. Women tend to be at higher risk for development of nevirapine-associated rash. For patients who interrupt VIRAMUNE XR dosing for more than 7 days and for whom restarting nevirapine therapy is not contraindicated, restart the recommended lead-in dosing with immediate-release VIRAMUNE using one 200 mg tablet daily (150 mg/m^2/day in pediatric patients) for the first 14 days [see Boxed Warning, Dosage and Administration (2.5), and Warnings and Precautions (5.2)].

17.2 Administration

Inform patients to take VIRAMUNE XR every day as prescribed. Patients should not alter the dose without consulting their doctor. If a dose is missed, patients should take the next dose as soon as possible. However, if a dose is skipped, the patient should not double the next dose. Advise patients to report to their doctor the use of any other medications.

Instruct patients to swallow VIRAMUNE XR tablets whole. They must not be chewed, crushed, or divided.

VIRAMUNE XR is not a cure for HIV-1 infection; patients may continue to experience illnesses associated with advanced HIV-1 infection, including opportunistic infections. Advise patients to remain under the care of a physician when using VIRAMUNE XR.

Patients should be told that sustained decreases in plasma HIV RNA have been associated with a reduced risk of progression to AIDS and death.

Patients should be advised to avoid doing things that can spread HIV-1 infection to others:

- Do not share needles or other injection equipment.
- Do not share personal items that can have blood or body fluids on them, like toothbrushes and razor blades.
- Do not have any kind of sex without protection. Always practice safe sex by using a latex or polyurethane condom to lower the chance of sexual contact with semen, vaginal secretions, or blood.
- Do not breastfeed. We do not know if VIRAMUNE XR can be passed to your baby in your breast milk and whether it could harm your baby. Also, mothers with HIV-1 should not breastfeed because HIV-1 can be passed to the baby in the breast milk.

Inform patients that they may occasionally see soft remnants of VIRAMUNE XR in their stool. These occurrences have not been shown to affect drug levels or response.

17.3 Drug Interactions

VIRAMUNE XR may interact with some drugs; therefore, patients should be advised to report to their doctor the use of any other prescription, non-prescription medication or herbal products, particularly St. John's wort [see Warnings and Precautions (5.4) and Drug Interactions (7)].

17.4 Contraceptives

Hormonal methods of birth control, other than depomedroxy-progesterone acetate (DMPA), should not be used as the sole method of contraception in women taking VIRAMUNE XR, since VIRAMUNE XR may lower the plasma levels of these medications. Additionally, when oral contraceptives are used for hormonal regulation during VIRAMUNE XR therapy, the therapeutic effect of the hormonal therapy should be monitored [see Drug Interactions (7)].

17.5 Methadone

VIRAMUNE XR may decrease plasma concentrations of methadone by increasing its hepatic metabolism. Narcotic withdrawal syndrome has been reported in patients treated with nevirapine and methadone concomitantly. Monitor methadone-maintained patients beginning nevirapine therapy for evidence of withdrawal and adjust methadone dose accordingly [see Drug Interactions (7)].

17.6 Fat Redistribution

Inform patients that redistribution or accumulation of body fat may occur in patients receiving antiretroviral therapy and that the cause and long-term health effects of these conditions are not known at this time [see Warnings and Precautions (5.6)].

Distributed by:
Boehringer Ingelheim Pharmaceuticals, Inc.
Ridgefield, CT 06877 USA

Copyright 2012 Boehringer Ingelheim Pharmaceuticals, Inc.
ALL RIGHTS RESERVED

IT5243GK142012
10006580/04

Distributed by:
Physicians Total Care, Inc.
Tulsa, OK 74146

MEDICATION GUIDE

VIRAMUNE® (VIH-rah-mune)
(nevirapine)
Tablets
VIRAMUNE® (VIH-rah-mune)
(nevirapine)
Oral Suspension
VIRAMUNE XR® (VIH-rah-mune)
(nevirapine)
Extended-Release Tablets

Read this Medication Guide before you start taking VIRAMUNE and each time you get a refill. There may be new information. This information does not take the place of talking to your doctor about your medical condition or treatment.

What is the most important information I should know about VIRAMUNE?

VIRAMUNE can cause serious side effects. These include severe liver and skin problems that can cause death. These problems can happen at any time during treatment, but your risk is higher during the first 18 weeks of treatment.
  1. Severe liver problems: Anyone who takes VIRAMUNE may get severe liver problems. In some cases these liver problems can lead to liver failure and the need for a liver transplant, or death.
    People who have a higher CD4^+ cell count when they begin VIRAMUNE treatment have a higher risk of liver problems, especially:
    - Women with CD4^+ counts higher than 250 cells/mm^3. This group has the highest risk.
    - Men with CD4^+ counts higher than 400 cells/mm^3.
      If you are a woman with CD4^+ counts higher than 250 cells/mm^3 or a man with CD4^+ counts higher than 400 cells/mm^3, you and your doctor will decide whether starting VIRAMUNE is right for you.
      In general, women have a higher risk of liver problems compared to men.
      People who have abnormal liver test results before starting VIRAMUNE treatment and people with hepatitis B or C also have a greater chance of getting liver problems.
      You may get a rash if you have liver problems.
    Stop taking VIRAMUNE and call your doctor right away if you have any of the following symptoms of liver problems:
    - dark (tea colored) urine
    - yellowing of your skin or whites of your eyes
    - light-colored bowel movements (stools)
    - fever
    - nausea (feeling sick to your stomach)
    - feel unwell or like you have the flu
    - pain or tenderness on your right side below your ribs
    - tiredness
    - loss of appetite
      Your doctor should see you and do blood tests often to check your liver function during the first 18 weeks of treatment with VIRAMUNE. You should continue to have your liver checked regularly during your treatment with VIRAMUNE. It is important for you to keep all of your doctor appointments.
  2. Severe rash and skin reactions: Skin rash is the most common side effect of VIRAMUNE. Most rashes happen in the first 6 weeks of taking VIRAMUNE. Rashes and skin reactions may be severe, life-threatening, and in some people, may lead to death. Stop using VIRAMUNE and call your doctor right away if you get a rash with any of the following symptoms:
    - blisters
    - mouth sores
    - red or inflamed eyes, like "pink eye" (conjunctivitis)
    - liver problems (see symptoms of liver problems above)
    - swelling of your face
    - fever
    - feel unwell or like you have the flu
    - tiredness
    - muscle or joint aches
    If your doctor tells you to stop treatment with VIRAMUNE because you have had any of the serious liver or skin problems described above, you should never take VIRAMUNE again.
    See the section "What are the possible side effects of VIRAMUNE?" for more information.

What is VIRAMUNE?

- VIRAMUNE tablets and VIRAMUNE oral solution are prescription HIV medicines used with other HIV medicines to treat HIV (Human Immunodeficiency Virus). HIV is the virus that causes AIDS (Acquired Immune Deficiency Syndrome).
- VIRAMUNE XR extended-release tablets are a prescription medicine used with other HIV medicines to treat HIV (Human Immunodeficiency Virus) in adults and in children who are 6 years of age to less than 18 years of age.
- VIRAMUNE and VIRAMUNE XR are a type of HIV medicine called a non-nucleoside reverse transcriptase inhibitor (NNRTI).

VIRAMUNE XR extended-release tablets are not for use in children less than 6 years of age.

When used with other HIV medicines, VIRAMUNE may:

1. Reduce the amount of HIV in your blood (called “viral load”)
2. Help increase the number of CD4 (T) cells in your blood which help fight off other infections.

Reducing the amount of HIV and increasing the CD4 (T) cell count may improve your immune system. This may reduce your risk of death or infections that can happen when your immune system is weak (opportunistic infections).

VIRAMUNE does not cure HIV infection or AIDS.
VIRAMUNE does not cure HIV or AIDS and you may continue to experience illnesses associated with HIV-1 infection, including opportunistic infections. You should remain under the care of a doctor when using VIRAMUNE.

You must stay on continuous HIV therapy to control HIV infection and decrease HIV-related illnesses.
  Avoid doing things that can spread HIV-1 infection to others:
  - Do not share needles or other injection equipment.
  - Do not share personal items that can have blood or body fluids on them, like toothbrushes and razor blades.
  - Do not have any kind of sex without protection. Always practice safe sex by using a latex or polyurethane condom to lower the chance of sexual contact with semen, vaginal secretions, or blood.
Ask your doctor if you have any questions on how to prevent passing HIV to other people.

Who should not take VIRAMUNE?

Tell your doctor if you have or have had liver problems. Your doctor may tell you not to take VIRAMUNE if you have certain liver problems.
VIRAMUNE is only for people diagnosed with HIV. If you have not been diagnosed as HIV positive, then do not take VIRAMUNE.

What should I tell my doctor before taking VIRAMUNE?

Before you take VIRAMUNE, tell your doctor if you:
  - have or have had hepatitis (inflammation of your liver) or problems with your liver. See "What is the most important information I should know about VIRAMUNE?" and "Who should not take VIRAMUNE?"
  - receive dialysis
  - have skin problems, such as a rash
  - or your child has trouble swallowing pills
  - have any other medical conditions
  - are pregnant or plan to become pregnant. It is not known if VIRAMUNE will harm your unborn baby.
    Pregnancy Registry: There is a pregnancy registry for women who take antiviral medicines during pregnancy. The purpose of the registry is to collect information about the health of you and your baby. Talk to your doctor about how you can take part in this registry.
  - are breast-feeding or plan to breast-feed. VIRAMUNE can pass into your breast milk and may harm your baby. You should not breastfeed if you have HIV because of the risk of passing HIV to your baby. Do not breast-feed during treatment with VIRAMUNE. Talk to your doctor about the best way to feed your baby.
Tell your doctor and pharmacist about all the medicines you take, including prescription and non-prescription medicines, vitamins and herbal supplements. VIRAMUNE may affect the way other medicines work, and other medicines may affect how VIRAMUNE works.
  You should not take VIRAMUNE if you also take:
    - St. John's Wort. St. John's Wort can lower the amount of VIRAMUNE in your body.
    - efavirenz (Sustiva®, Atripla®) , etravirine (Intelence®), rilpivirine (Edurant® Complera®), or delavirdine (Rescriptor®).
    - atazanavir (Reyataz®)
    - lopinavir and ritonavir (Kaletra®) once daily
    - fosamprenavir calcium (Lexiva®) without ritonavir (Norvir®)
    - itraconazole (Sporanox®)
    - ketoconazole (Nizoral®)
    - rifampin (Rifadin®, Rifamate®, Rifater®)
    - Birth control pills. Birth control pills taken by mouth (oral contraceptives) and other hormone types of birth control may not work to prevent pregnancy. Talk with your doctor about other types of birth control that you can use to prevent pregnancy during treatment with VIRAMUNE.
  Also tell your doctor if you take:
    - clarithromycin (Biaxin®)
    - fluconazole (Diflucan®)
    - indinavir sulfate (Crixivan®)
    - methadone
    - nelfinavir mesylate (Viracept®)
    - rifabutin (Mycobutin®)
    - warfarin (Coumadin®, Jantoven®)
    - saquinavir mesylate (Invirase®)
    - amiodarone, disopyramide (Norpace®), lidocaine
    - carbamazepine, clonazepam (Klonopin®), ethosuximide (Zarontin®)
    - diltiazem, nifedipine, verapamil
    - cyclophosphamide
    - ergotamine
    - cyclosporine, tacrolimus, sirolimus (Rapamune®)
    - cisapride (Propulsid®)
    - fentanyl
If you are not sure if you take a medicine above, ask your doctor or pharmacist.
Know the medicines you take. Keep a list of them to show your doctor or pharmacist when you get a new medicine.

How should I take VIRAMUNE?

- VIRAMUNE is always taken in combination with other anti-HIV medications.
- VIRAMUNE comes in 3 different forms. Your doctor will prescribe the form of VIRAMUNE that is right for you.
  - VIRAMUNE tablets
  - VIRAMUNE oral suspension
  - VIRAMUNE XR extended-release tablets
- Take VIRAMUNE exactly as your doctor tells you to take it. Do not change your dose unless your doctor tells you to.
- You should never take more than one form of VIRAMUNE at the same time. Talk to your doctor if you have any questions.
- If your child is prescribed VIRAMUNE, your child’s doctor will tell you exactly how VIRAMUNE should be taken.
- Swallow VIRAMUNE XR extended-release tablets whole. Do not chew, crush, or divide VIRAMUNE XR extended-release tablets.
- Do not crush or chew VIRAMUNE XR extended-release tablets.
- You may take VIRAMUNE with or without food.
- Do not miss a dose of VIRAMUNE. If you miss a dose of VIRAMUNE, take the missed dose as soon as you remember. If it is almost time for your next dose, do not take the missed dose, just take the next dose at your regular time. Do not take two doses at the same time.
- If you stop taking VIRAMUNE for more than 7 days, ask your doctor how much to take before you start taking it again. You may need to begin taking the VIRAMUNE starting dose again, which is taken 1 time each day for 14 days.

Starting VIRAMUNE tablets:
1. Your doctor should start you with 1 dose each day to lower your chance of getting a serious rash. It is important that you only take 1 dose of VIRAMUNE each day for the first 14 days.
  - Call your doctor right away if you get a skin rash during the first 14 days of VIRAMUNE treatment.
  - Do not increase your dose to 2 times a day if you have a rash.
  - You should never take your starting dose for longer than 28 days. If after 28 days you are still receiving this starting dose because you have a rash, you and your doctor should talk about prescribing another HIV medicine for you instead of VIRAMUNE.
2. Day 15, you will take 1 VIRAMUNE tablet two times a day.

Starting VIRAMUNE XR extended-release tablets when this is the first time you are taking any form of VIRAMUNE:
1. Your doctor should start you with 1 dose of VIRAMUNE tablets or oral suspension each day to lower your chance of getting a serious rash. It is important that you only take 1 dose of VIRAMUNE each day for the first 14 days.
  - Call your doctor right away if you get a skin rash during the first 14 days of VIRAMUNE treatment.
  - You should never take your starting dose for longer than 28 days. If after 28 days you are still receiving this starting dose because you have a rash, you and your doctor should talk about prescribing another HIV medicine for you instead of VIRAMUNE.
  - Do not start VIRAMUNE XR extended-release tablets if you have a rash.
2. Day 15, take VIRAMUNE XR 1 time a day as prescribed by your doctor.

Switching from VIRAMUNE tablets or oral suspension to VIRAMUNE XR extended-release tablets:
Take VIRAMUNE XR 1 time a day as prescribed by your doctor.

You may sometimes pass a soft mass in your stools (bowel movement) that looks like your VIRAMUNE XR extended-release tablets. This will not affect the way your medicine works.

If you take VIRAMUNE Oral Suspension:
- If you or your child takes VIRAMUNE suspension (liquid), shake it gently before each use. Use an oral dosing syringe or dosing cup to measure the right dose. The oral dosing syringe and dosing cup are not provided with VIRAMUNE Suspension. Ask your pharmacist for a syringe or cup if you do not have one.
- After drinking the medicine, fill the dosing cup with water and drink it to make sure you get all the medicine.
- If the dose is less than 1 teaspoon (5 mL), use the syringe instead of the dosing cup.

What are the possible side effects of VIRAMUNE?

VIRAMUNE may cause serious side effects, including:
  - See "What is the most important information I should know about VIRAMUNE?"
    - Changes in your immune system (Immune Reconstitution Syndrome) can happen when you start taking HIV medicines. Your immune system may get stronger and begin to fight infections that have been hidden in your body for a long time. Tell your doctor if you start having new symptoms after starting your HIV medicine.
    - Changes in body fat can happen in some people who take antiretroviral therapy. These changes may include increased amount of fat in the upper back and neck ("buffalo hump"), breast, and around the middle of your body (trunk). Loss of fat from your legs, arms, and face can also happen. The cause and long-term health effects of these problems are not known at this time.

The most common side effect of VIRAMUNE is rash.
Tell your doctor if you have any side effect that bothers you or that does not go away.
These are not all the possible side effects of VIRAMUNE. For more information, ask your doctor or pharmacist.
Call your doctor for medical advice about side effects. You may report side effects to FDA at 1-800-FDA-1088.

How should I store VIRAMUNE?

- Store VIRAMUNE at room temperature between 59°F to 86°F (15°C to 30°C).
- Throw away VIRAMUNE that is no longer needed or out-of-date.

Keep VIRAMUNE and all medicines out of the reach of children.

General information about VIRAMUNE.

Medicines are sometimes prescribed for purposes other than those listed in a Medication Guide. Do not use VIRAMUNE for a condition for which it was not prescribed. Do not give VIRAMUNE to other people, even if they have the same condition you have. It may harm them.

This Medication Guide summarizes the most important information about VIRAMUNE. If you would like more information, talk with your doctor. You can ask your pharmacist or doctor for information about VIRAMUNE that is written for health professionals.

For more information, go to www.viramune.com or www.viramunexr.com or call Boehringer Ingelheim Pharmaceuticals, Inc., at 1-800-542-6257, or (TTY) 1-800-459-9906.

What are the ingredients in VIRAMUNE?

Active ingredient: nevirapine
  Inactive ingredients:
  VIRAMUNE Tablets: microcrystalline cellulose, lactose monohydrate, povidone, sodium starch glycolate, colloidal silicon dioxide, and magnesium stearate
  VIRAMUNE Oral Suspension: carbomer 934P, methylparaben, propylparaben, sorbitol, sucrose, polysorbate 80, sodium hydroxide, and purified water
  VIRAMUNE XR Tablets: lactose monohydrate, hypromellose, iron oxide, and magnesium stearate

This Medication Guide has been approved by the U.S. Food and Drug Administration

Distributed by:
Boehringer Ingelheim Pharmaceuticals, Inc.
Ridgefield, CT 06877 USA

Revised: November 2012

The brands listed are trademarks of their respective owners and are not trademarks of Boehringer Ingelheim Pharmaceuticals, Inc. The makers of these brands are not affiliated with and do not endorse Boehringer Ingelheim Pharmaceuticals, Inc., or its products.

Copyright 2012 Boehringer Ingelheim Pharmaceuticals, Inc.
ALL RIGHTS RESERVED

IT5243GK142012
10006580/04

PACKAGE LABEL

VIRAMUNE XR tablets, 400 mg